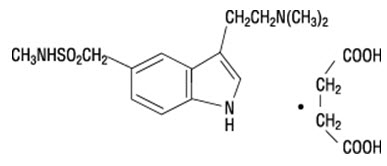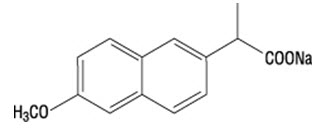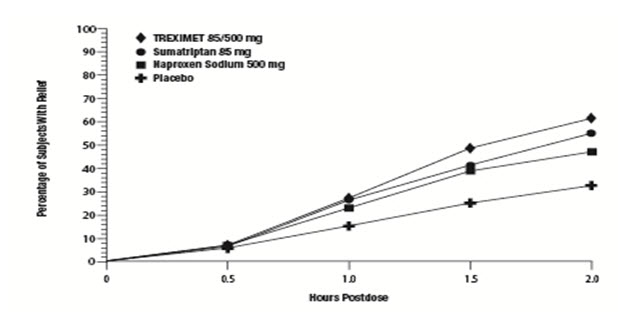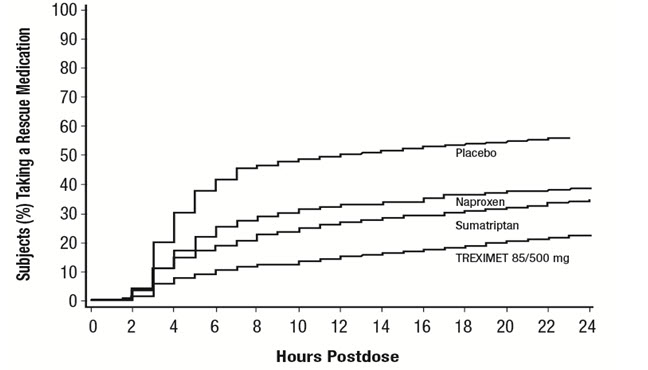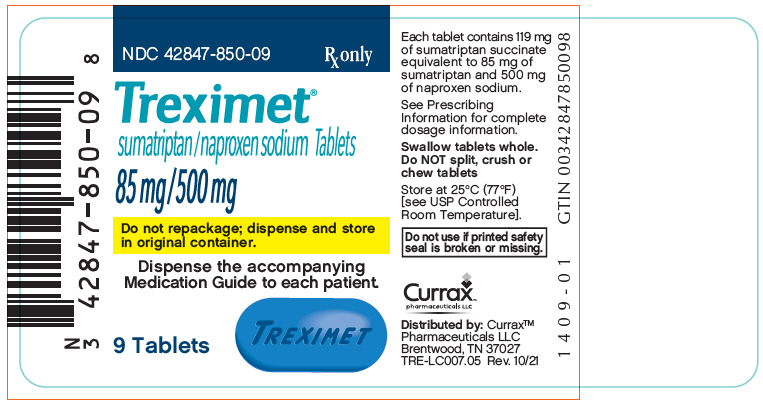 DRUG LABEL: Treximet
NDC: 42847-850 | Form: TABLET, FILM COATED
Manufacturer: Currax Pharmaceuticals LLC
Category: prescription | Type: HUMAN PRESCRIPTION DRUG LABEL
Date: 20241223

ACTIVE INGREDIENTS: Sumatriptan Succinate 85 mg/1 1; Naproxen Sodium 500 mg/1 1
INACTIVE INGREDIENTS: Croscarmellose Sodium; ANHYDROUS DIBASIC CALCIUM PHOSPHATE; FD&C BLUE NO. 2; Magnesium Stearate; MICROCRYSTALLINE CELLULOSE; POVIDONE, UNSPECIFIED; Sodium Bicarbonate; Talc; HYPROMELLOSE, UNSPECIFIED; Triacetin; Titanium Dioxide

HIGHLIGHTS OF PRESCRIBING INFORMATION

These highlights do not include all the information needed to use TREXIMET safely and effectively. See full prescribing information for TREXIMET.
TREXIMET (sumatriptan and naproxen sodium) tablets, for oral use
Initial U.S. Approval: 2008

WARNING: RISK OF SERIOUS CARDIOVASCULAR AND GASTROINTESTINAL EVENTS

See full prescribing information for complete boxed warning.

- Nonsteroidal anti-inflammatory drugs (NSAIDs) cause an increased risk of serious cardiovascular thrombotic events, including myocardial infarction and stroke, which can be fatal. This risk may occur early in treatment and may increase with duration of use. (5.1)
- TREXIMET is contraindicated in the setting of coronary artery bypass graft (CABG) surgery (4, 5.1)
- NSAIDs cause an increased risk of serious gastrointestinal (GI) adverse events including bleeding, ulceration, and perforation of the stomach or intestines, which can be fatal. These events can occur at any time during use and without warning symptoms. Elderly patients and patients with a prior history of peptic ulcer disease and/or GI bleeding are at greater risk for serious GI events. (5.2)

RECENT MAJOR CHANGES

Warnings and Precautions (5.14) | 11/2024

1 INDICATIONS AND USAGE

TREXIMET is a combination of sumatriptan, a serotonin (5-HT) 1b/1d receptor agonist (triptan), and naproxen sodium, a non-steroidal anti-inflammatory drug, indicated for the acute treatment of migraine with or without aura in adults and pediatric patients 12 years of age and older. (1)

Limitations of Use:

- Use only if a clear diagnosis of migraine headache has been established. (1)
- Not indicated for the prophylactic therapy of migraine attacks. (1)
- Not indicated for the treatment of cluster headache. (1)

2 DOSAGE AND ADMINISTRATION

Adults

- Recommended dosage: 1 tablet of 85/500 mg. (2.1)
- Maximum dosage in a 24-hour period: 2 tablets of 85/500 mg; separate doses by at least 2 hours. (2.1)

Pediatric Patients 12 to 17 years of Age

- Recommended dosage: 1 tablet of 10/60 mg. (2.2)
- Maximum dosage in a 24-hour period: 1 tablet of 85/500 mg.

Mild to Moderate Hepatic Impairment

- Recommended dosage: 1 tablet of 10/60 mg. (2.3, 8.7)

3 DOSAGE FORMS AND STRENGTHS

Tablets: | 85 mg sumatriptan / 500 mg naproxen sodium (3)
 | 10 mg sumatriptan / 60 mg naproxen sodium (3)

4 CONTRAINDICATIONS

- History of coronary artery disease or coronary vasospasm. (4)
- In the setting of CABG surgery. (4)
- Wolff-Parkinson-White syndrome or other cardiac accessory conduction pathway disorders. (4)
- History of stroke, transient ischemic attack, or hemiplegic or basilar migraine. (4)
- Peripheral vascular disease. (4)
- Ischemic bowel disease. (4)
- Uncontrolled hypertension. (4)
- Recent (within 24 hours) use of another 5-HT1 agonist (e.g., another triptan) or of ergotamine-containing medication. (4)
- Concurrent or recent (past 2 weeks) use of monoamine oxidase-A inhibitor. (4)
- History of asthma, urticaria, other allergic type reactions, rhinitis, or nasal polyps syndrome after taking aspirin or other NSAID/analgesic drugs. (4)
- Known hypersensitivity to sumatriptan, naproxen, or any components of TREXIMET (angioedema and anaphylaxis seen). (4)
- Severe hepatic impairment. (4)

5 WARNINGS AND PRECAUTIONS

- Cardiovascular Thrombotic Events: Perform cardiac evaluation in patients with cardiovascular risk factors. (5.1)
- Arrhythmias: Discontinue TREXIMET if occurs. (5.3)
- Chest, Throat, Neck, and/or Jaw Pain/Tightness/Pressure: Generally not associated with myocardial ischemia; evaluate for coronary artery disease in patients at high risk. (5.4)
- Cerebrovascular Events: Discontinue TREXIMET if occurs. (5.5)
- Other Vasospasm Reactions: Discontinue TREXIMET if non-coronary vasospastic reaction occurs. (5.6)
- Hepatotoxicity: Inform patients of warning signs and symptoms of hepatotoxicity. Discontinue if abnormal liver tests persist or worsen or if clinical signs and symptoms of liver disease develop. (5.7)
- Hypertension: Patients taking some antihypertensive medications may have impaired response to these therapies when taking NSAIDs. Monitor blood pressure. (5.8)
- Heart Failure and Edema: Avoid use of TREXIMET in patients with severe heart failure unless benefits are expected to outweigh risk of worsening heart failure. (5.9)
- Medication Overuse Headache: Detoxification may be necessary. (5.10)
- Serotonin Syndrome: Discontinue TREXIMET if occurs. (5.11)
- Renal Toxicity and Hyperkalemia: Monitor renal function in patients with renal or hepatic impairment, heart failure, dehydration, or hypovolemia. Avoid use of TREXIMET in patients with advanced renal disease. (5.12)
- Anaphylactic Reactions: TREXIMET should not be given to patients with the aspirin triad. Seek emergency help if an anaphylactic reaction occurs. (5.13)
- Serious Skin Reactions: Discontinue TREXIMET at first sign of rash or other signs of hypersensitivity. (5.14)
- Drug Reaction with Eosinophilia and Systemic Symptoms (DRESS): Discontinue and evaluate clinically. (5.15)
- Fetal Toxicity: Limit use of NSAIDs, including TREXIMET, between about 20 to 30 weeks in pregnancy due to the risk of oligohydramnios/fetal renal dysfunction. Avoid use of NSAIDs in women at about 30 weeks gestation and later in pregnancy due to the risks of oligohydramnios/fetal renal dysfunction and premature closure of the fetal ductus arteriosus. (5.16, 8.1)
- Hematologic Toxicity: Monitor hemoglobin or hematocrit in patients with any signs or symptoms of anemia. (5.17)
- Exacerbation of Asthma Related to Aspirin Sensitivity: TREXIMET is contraindicated in patients with aspirin-sensitive asthma. Monitor patients with preexisting asthma (without aspirin sensitivity). (5.18)

6 ADVERSE REACTIONS

The most common adverse reactions (incidence ≥2%) were:

- Adults: Dizziness, somnolence, nausea, chest discomfort/chest pain, neck/throat/jaw pain/tightness/pressure, paresthesia, dyspepsia, dry mouth. (6.1)
- Pediatrics: Hot flush (i.e., hot flash[es]) and muscle tightness. (6.1)

To report SUSPECTED ADVERSE REACTIONS, contact Currax Pharmaceuticals LLC at 1-800-793-2145 or FDA at 1-800-FDA-1088 or www.fda.gov/medwatch.

7 DRUG INTERACTIONS

- Drugs that Interfere with Hemostasis (e.g. warfarin, aspirin, SSRIs/SNRIs): Monitor patients for bleeding who are concomitantly taking TREXIMET with drugs that interfere with hemostasis. Concomitant use of TREXIMET and analgesic doses of aspirin is not generally recommended. (7.1)
- ACE Inhibitors and ARBs: Concomitant use with TREXIMET in elderly, volume depleted, or those with renal impairment may result in deterioration of renal function. In such high risk patients, monitor for signs of worsening renal function. (7.1)
- Diuretics: NSAIDs can reduce natriuretic effect of loop and thiazide diuretics. Monitor patients to assure diuretic efficacy including antihypertensive effects. (7.1)
- Digoxin: Concomitant use with TREXIMET can increase serum concentration and prolong half-life of digoxin. Monitor serum digoxin levels. (7.1)
- Lithium: Increases lithium plasma levels. (7.1)
- Methotrexate: Increases methotrexate plasma levels. (7.1)

8 USE IN SPECIFIC POPULATIONS

- Infertility: NSAIDs are associated with reversible infertility. Consider withdrawal of TREXIMET in women who have difficulties conceiving (8.3)

FULL PRESCRIBING INFORMATION

WARNING: RISK OF SERIOUS CARDIOVASCULAR AND GASTROINTESTINAL EVENTS

Cardiovascular Thrombotic Events

- Nonsteroidal anti-inflammatory drugs (NSAIDs) cause an increased risk of serious cardiovascular thrombotic events, including myocardial infarction and stroke, which can be fatal. This risk may occur early in treatment and may increase with duration of use [see Warnings and Precautions (5.1)].
- TREXIMET is contraindicated in the setting of coronary artery bypass graft (CABG) surgery [see Contraindications (4) Warnings and Precautions (5.1)].

Gastrointestinal Bleeding, Ulceration, and Perforation

- NSAIDs cause an increased risk of serious gastrointestinal (GI) adverse events including bleeding, ulceration, and perforation of the stomach or intestines, which can be fatal. These events can occur at any time during use and without warning symptoms. Elderly patients and patients with a prior history of peptic ulcer disease and/or GI bleeding are at greater risk for serious GI events [see Warnings and Precautions (5.2)].

1 INDICATIONS AND USAGE

TREXIMET is indicated for the acute treatment of migraine with or without aura in adults and pediatric patients 12 years of age and older.

Limitations of Use:

- Use only if a clear diagnosis of migraine headache has been established. If a patient has no response to the first migraine attack treated with TREXIMET, reconsider the diagnosis of migraine before TREXIMET is administered to treat any subsequent attacks.
- TREXIMET is not indicated for the prevention of migraine attacks.
- Safety and effectiveness of TREXIMET have not been established for cluster headache.

2 DOSAGE AND ADMINISTRATION

2.1 Dosage in Adults

The recommended dosage for adults is 1 tablet of TREXIMET 85/500 mg. TREXIMET 85/500 mg contains a dose of sumatriptan higher than the lowest effective dose. The choice of the dose of sumatriptan, and of the use of a fixed combination such as in TREXIMET 85/500 mg should be made on an individual basis, weighing the possible benefit of a higher dose of sumatriptan with the potential for a greater risk of adverse reactions.

The maximum recommended dosage in a 24-hour period is 2 tablets, taken at least 2 hours apart.

The safety of treating an average of more than 5 migraine headaches in adults in a 30-day period has not been established.

Use the lowest effective dosage for the shortest duration consistent with individual patient treatment goals [see Warnings and Precautions (5)].

2.2 Dosage in Pediatric Patients 12 to 17 Years of Age

The recommended dosage for pediatric patients 12 to 17 years of age is 1 tablet of TREXIMET 10/60 mg.

The maximum recommended dosage in a 24-hour period is 1 tablet of TREXIMET 85/500 mg.

The safety of treating an average of more than 2 migraine headaches in pediatric patients in a 30-day period has not been established.

Use the lowest effective dosage for the shortest duration consistent with individual patient treatment goals [see Warnings and Precautions (5)].

2.3 Dosing in Patients with Hepatic Impairment

TREXIMET is contraindicated in patients with severe hepatic impairment [see Contraindications (4), Use in Specific Populations (8.7), Clinical Pharmacology (12.3)].

In patients with mild to moderate hepatic impairment, the recommended dosage in a 24-hour period is 1 tablet of TREXIMET 10/60 mg [see Use in Specific Populations (8.7), Clinical Pharmacology (12.3)].

Use the lowest effective dosage for the shortest duration consistent with individual patient treatment goals [see Warnings and Precautions (5)].

2.4 Administration Information

TREXIMET may be administered with or without food. Tablets should not be split, crushed, or chewed.

3 DOSAGE FORMS AND STRENGTHS

10 mg sumatriptan/60 mg naproxen sodium, light-blue film-coated tablets, debossed on one side with "TREXIMET" and the other side with "10-60".

85 mg sumatriptan/500 mg naproxen sodium, blue film-coated tablets, debossed on one side with "TREXIMET"

4 CONTRAINDICATIONS

TREXIMET is contraindicated in the following patients:

- Ischemic coronary artery disease (CAD) (angina pectoris, history of myocardial infarction, or documented silent ischemia) or coronary artery vasospasm, including Prinzmetal's angina [see Warnings and Precautions (5.1)].
- In the setting of coronary artery bypass graft (CABG) surgery [see Warnings and Precautions (5.1)].
- Wolff-Parkinson-White syndrome or arrhythmias associated with other cardiac accessory conduction pathway disorders [see Warnings and Precautions (5.3)].
- History of stroke or transient ischemic attack (TIA) or history of hemiplegic or basilar migraine because these patients are at a higher risk of stroke [see Warnings and Precautions (5.5)].
- Peripheral vascular disease [see Warnings and Precautions (5.6)].
- Ischemic bowel disease [see Warnings and Precautions (5.6)].
- Uncontrolled hypertension [see Warnings and Precautions (5.8)].
- Recent use (i.e., within 24 hours) of ergotamine-containing medication, ergot-type medication (such as dihydroergotamine or methysergide), or another 5-hydroxytryptamine1 (5-HT1) agonist [see Drug Interactions (7)].
- Concurrent administration of a monoamine oxidase (MAO)-A inhibitor or recent (within 2 weeks) use of an MAO-A inhibitor [see Drug Interactions (7), Clinical Pharmacology (12.3)].
- History of asthma, urticaria, or allergic-type reactions after taking aspirin or other NSAIDs. Severe, sometimes fatal, anaphylactic reactions to NSAIDs have been reported in such patients [see Warnings and Precautions (5.13, 5.14, 5.18)].
- Known hypersensitivity (e.g., anaphylactic reactions, angioedema, and serious skin reactions) to sumatriptan, naproxen, or any components of TREXIMET [see Warnings and Precautions (5.14)].
- Severe hepatic impairment [see Warnings and Precautions (5.7), Use in Specific Populations (8.7), Clinical Pharmacology (12.3)].

5 WARNINGS AND PRECAUTIONS

5.1 Cardiovascular Thrombotic Events

The use of TREXIMET is contraindicated in patients with ischemic or vasospastic coronary artery disease (CAD) and in the setting of coronary artery bypass graft (CABG) surgery due to increased risk of serious cardiovascular events with sumatriptan and NSAIDS [see Contraindications (4)].

Cardiovascular Events with Sumatriptan

There have been rare reports of serious cardiac adverse reactions, including acute myocardial infarction, occurring within a few hours following administration of sumatriptan. Some of these reactions occurred in patients without known CAD. TREXIMET may cause coronary artery vasospasm (Prinzmetal's angina), even in patients without a history of CAD.

Cardiovascular Thrombotic Events with Nonsteroidal Anti-inflammatory Drugs

Clinical trials of several COX-2 selective and nonselective NSAIDs of up to three years duration have shown an increased risk of serious cardiovascular (CV) thrombotic events, including myocardial infarction (MI) and stroke, which can be fatal. Based on available data, it is unclear that the risk for CV thrombotic events is similar for all NSAIDs. The relative increase in serious CV thrombotic events over baseline conferred by NSAID use appears to be similar in those with and without known CV disease or risk factors for CV disease. However, patients with known CV disease or risk factors had a higher absolute incidence of excess serious CV thrombotic events, due to their increased baseline rate. Some observational studies found that this increased risk of serious CV thrombotic events began as early as the first weeks of treatment. The increase in CV thrombotic risk has been observed most consistently at higher doses.

To minimize the potential risk for an adverse CV event in NSAID-treated patients, use the lowest effective dose for the shortest duration possible. Physicians and patients should remain alert for the development of such events, throughout the entire treatment course, even in the absence of previous CV symptoms. Patients should be informed about the symptoms of serious CV events and the steps to take if they occur.

There is no consistent evidence that concurrent use of aspirin mitigates the increased risk of serious CV thrombotic events associated with NSAID use. The concurrent use of aspirin and an NSAID, such as naproxen, increases the risk of serious gastrointestinal (GI) events [see Warnings and Precautions (5.2)].

Status Post Coronary Artery Bypass Graft (CABG) Surgery

Two large, controlled clinical trials of a COX-2 selective NSAID for the treatment of pain in the first 10–14 days following CABG surgery found an increased incidence of myocardial infarction and stroke. NSAIDs are contraindicated in the setting of CABG [see Contraindications (4)].

Post-MI Patients

Observational studies conducted in the Danish National Registry have demonstrated that patients treated with NSAIDs in the post-MI period were at increased risk of reinfarction, CV-related death, and all-cause mortality beginning in the first week of treatment. In this same cohort, the incidence of death in the first year post-MI was 20 per 100 person years in NSAID-treated patients compared to 12 per 100 person years in non-NSAID exposed patients. Although the absolute rate of death declined somewhat after the first year post-MI, the increased relative risk of death in NSAID users persisted over at least the next four years of follow-up.

Perform a cardiovascular evaluation in patients who have multiple cardiovascular risk factors (e.g., increased age, diabetes, hypertension, smoking, obesity, strong family history of CAD) prior to receiving TREXIMET. If there is evidence of CAD or coronary artery vasospasm, TREXIMET is contraindicated. For patients with multiple cardiovascular risk factors who have a negative cardiovascular evaluation, consider administering the first dose of TREXIMET in a medically supervised setting and performing an electrocardiogram (ECG) immediately following administration of TREXIMET. For such patients, consider periodic cardiovascular evaluation in intermittent long-term users of TREXIMET.

Physicians and patients should remain alert for the development of cardiovascular events, even in the absence of previous cardiovascular symptoms. Patients should be informed about the signs and/or symptoms of serious cardiovascular events and the steps to take if they occur.

5.2 Gastrointestinal Bleeding, Ulceration, and Perforation

NSAIDs, including naproxen, a component of TREXIMET, cause serious gastrointestinal adverse events including inflammation, bleeding, ulceration, and perforation of the stomach, small intestine, or large intestine, which can be fatal. These serious adverse events can occur at any time, with or without warning symptoms, in patients treated with NSAIDs. Only 1 in 5 patients who develop a serious upper gastrointestinal adverse event on NSAID therapy is symptomatic. Upper gastrointestinal ulcers, gross bleeding, or perforation caused by NSAIDs appear to occur in approximately 1% of patients treated daily for 3 to 6 months and in about 2% to 4% of patients treated for 1 year. However, even short-term therapy is not without risk.

Among 3,302 adult patients with migraine who received TREXIMET in controlled and uncontrolled clinical trials, 1 patient experienced a recurrence of gastric ulcer after taking 8 doses over 3 weeks, and 1 patient developed a gastric ulcer after treating an average of 8 attacks per month over 7 months.

Risk Factors for GI Bleeding, Ulceration, and Perforation

Patients with a prior history of peptic ulcer disease and/or gastrointestinal bleeding who use NSAIDs have a greater than 10-fold increased risk for developing gastrointestinal bleeding compared with patients with neither of these risk factors. Other factors that increase the risk for gastrointestinal bleeding in patients treated with NSAIDs include longer duration of NSAID therapy; concomitant use of oral corticosteroids, aspirin, anticoagulants, or selective serotonin reuptake inhibitors (SSRIs); smoking; use of alcohol; older age; and poor general health status. Most postmarketing reports of fatal gastrointestinal events occurred in elderly or debilitated patients, and therefore special care should be taken in treating this population. Additionally, patients with advanced liver disease and/or coagulopathy are at increased risk for GI bleeding.

Strategies to Minimize the GI Risks in NSAID-treated patients:

- Use the lowest effective dosage for the shortest possible duration.
- Avoid administration of more than one NSAID at a time.
- Avoid use in patients at higher risk unless benefits are expected to outweigh the increased risk of bleeding. For high risk patients, as well as those with active GI bleeding, consider alternate therapies other than NSAIDs.
- Remain alert for signs and symptoms of GI ulceration and bleeding during NSAID therapy.
- If a serious GI adverse event is suspected, promptly initiate evaluation and treatment, and discontinue TREXIMET until a serious GI adverse event is ruled out.
- In the setting of concomitant use of low-dose aspirin for cardiac prophylaxis, monitor patients more closely for evidence of GI bleeding [see Drug Interactions (7)].

5.3 Arrhythmias

Life-threatening disturbances of cardiac rhythm, including ventricular tachycardia and ventricular fibrillation leading to death, have been reported within a few hours following the administration of 5-HT1 agonists. Discontinue TREXIMET if these disturbances occur. TREXIMET is contraindicated in patients with Wolff-Parkinson-White syndrome or arrhythmias associated with other cardiac accessory conduction pathway disorders.

5.4 Chest, Throat, Neck, and/or Jaw Pain/Tightness/Pressure

Sensations of tightness, pain, pressure, and heaviness in the precordium, throat, neck, and jaw commonly occur after treatment with sumatriptan and are usually non-cardiac in origin. However, perform a cardiac evaluation if these patients are at high cardiac risk. The use of TREXIMET is contraindicated in patients with CAD and those with Prinzmetal's variant angina.

5.5 Cerebrovascular Events

Cerebral hemorrhage, subarachnoid hemorrhage, and stroke have occurred in patients treated with 5-HT1 agonists, and some have resulted in fatalities. In a number of cases, it appears possible that the cerebrovascular events were primary, the 5-HT1 agonist having been administered in the incorrect belief that the symptoms experienced were a consequence of migraine when they were not. Also, patients with migraine may be at increased risk of certain cerebrovascular events (e.g., stroke, hemorrhage, TIA). Discontinue TREXIMET if a cerebrovascular event occurs.

Before treating headaches in patients not previously diagnosed as migraineurs, and in migraineurs who present with atypical symptoms, exclude other potentially serious neurological conditions. TREXIMET is contraindicated in patients with a history of stroke or TIA [see Contraindications (4)].

5.6 Other Vasospasm Reactions

Sumatriptan may cause non-coronary vasospastic reactions, such as peripheral vascular ischemia, gastrointestinal vascular ischemia and infarction (presenting with abdominal pain and bloody diarrhea), splenic infarction, and Raynaud′s syndrome. In patients who experience symptoms or signs suggestive of non-coronary vasospasm reaction following the use of any 5-HT1 agonist, rule out a vasospastic reaction before receiving additional TREXIMET.

Reports of transient and permanent blindness and significant partial vision loss have been reported with the use of 5-HT1 agonists. Since visual disorders may be part of a migraine attack, a causal relationship between these events and the use of 5-HT1 agonists have not been clearly established.

5.7 Hepatotoxicity

Borderline elevations of 1 or more liver tests may occur in up to 15% of patients who take NSAIDs including naproxen, a component of TREXIMET. Hepatic abnormalities may be the result of hypersensitivity rather than direct toxicity. These abnormalities may progress, may remain essentially unchanged, or may be transient with continued therapy. Notable (3 times the upper limit of normal) elevations of SGPT (ALT) or SGOT (AST) have been reported in approximately 1% of patients in clinical trials with NSAIDs. In addition, rare, sometimes fatal cases of severe hepatic injury, including jaundice and fatal fulminant hepatitis, liver necrosis, and hepatic failure have been reported with NSAIDs.

TREXIMET is contraindicated in patients with severe hepatic impairment [see Use in Specific Populations (8.7), Clinical Pharmacology (12.3)]. A patient with symptoms and/or signs suggesting liver dysfunction, or in whom an abnormal liver test has occurred, should be evaluated for evidence of the development of a more severe hepatic reaction while on therapy with TREXIMET. TREXIMET should be discontinued if clinical signs and symptoms consistent with liver disease develop, if systemic manifestations occur (e.g., eosinophilia, rash), or if abnormal liver tests persist or worsen.

Inform patients of the warning signs and symptoms of hepatotoxicity (e.g., nausea, fatigue, lethargy, diarrhea, pruritus, jaundice, right upper quadrant tenderness, and "flulike" symptoms). If clinical signs and symptoms consistent with liver disease develop, or if systemic manifestations occur (e.g., eosinophilia, rash, etc.), discontinue TREXIMET immediately, and perform a clinical evaluation of the patient.

5.8 Hypertension

Significant elevation in blood pressure, including hypertensive crisis with acute impairment of organ systems, has been reported on rare occasions in patients treated with 5-HT1 agonists, including sumatriptan, a component of TREXIMET. This occurrence has included patients without a history of hypertension.

NSAIDs, including naproxen, a component of TREXIMET, can also lead to onset of new hypertension or worsening of preexisting hypertension, either of which may contribute to the increased incidence of cardiovascular events. Patients taking angiotensin converting enzyme (ACE) inhibitors, angiotensin receptor blockers (ARBs), beta-blockers, thiazide diuretics, or loop diuretics may have impaired response to these therapies when taking NSAIDs [see Drug Interactions (7)].

Monitor blood pressure in patients treated with TREXIMET. TREXIMET is contraindicated in patients with uncontrolled hypertension [see Contraindications (4)].

5.9 Heart Failure and Edema

The Coxib and traditional NSAID Trialists' Collaboration meta-analysis of randomized controlled trials demonstrated an approximately two-fold increase in hospitalizations for heart failure in COX-2 selective-treated patients and nonselective NSAID-treated patients compared to placebo-treated patients. In a Danish National Registry study of patients with heart failure, NSAID use increased the risk of MI, hospitalization for heart failure, and death.

Additionally, fluid retention and edema have been observed in some patients treated with NSAIDs. Use of naproxen may blunt the CV effects of several therapeutic agents used to treat these medical conditions (e.g., diuretics, ACE inhibitors, or angiotensin receptor blockers [ARBs]) [see Drug Interactions (7)].

Avoid the use of TREXIMET in patients with severe heart failure unless the benefits are expected to outweigh the risk of worsening heart failure. If TREXIMET is used in patients with severe heart failure, monitor patients for signs of worsening heart failure.

Since each TREXIMET 85/500 mg tablet contains approximately 60 mg of sodium and each TREXIMET 10/60 mg tablet contains approximately 20 mg of sodium, this should be considered in patients whose overall intake of sodium must be severely restricted.

5.10 Medication Overuse Headache

Overuse of acute migraine drugs (e.g., ergotamine, triptans, opioids, or a combination of these drugs for 10 or more days per month) may lead to exacerbation of headache (medication overuse headache). Medication overuse headache may present as migraine-like daily headaches, or as a marked increase in frequency of migraine attacks. Detoxification of patients, including withdrawal of the overused drugs, and treatment of withdrawal symptoms (which often includes a transient worsening of headache) may be necessary.

5.11 Serotonin Syndrome

Serotonin syndrome may occur with TREXIMET, particularly during coadministration with selective serotonin reuptake inhibitors (SSRIs), serotonin norepinephrine reuptake inhibitors (SNRIs), tricyclic antidepressants (TCAs), and MAO inhibitors [see Contraindications (4) and Drug Interactions (7.1)]. Serotonin syndrome symptoms may include mental status changes (e.g., agitation, hallucinations, coma), autonomic instability (e.g., tachycardia, labile blood pressure, hyperthermia), neuromuscular aberrations (e.g., hyperreflexia, incoordination), and/or gastrointestinal symptoms (e.g., nausea, vomiting, diarrhea). The onset of symptoms usually occurs within minutes to hours of receiving a new or a greater dose of a serotonergic medication. Discontinue TREXIMET if serotonin syndrome is suspected.

5.12 Renal Toxicity and Hyperkalemia

Renal Toxicity

Long-term administration of NSAIDs has resulted in renal papillary necrosis and other renal injury. Renal toxicity has also been seen in patients in whom renal prostaglandins have a compensatory role in the maintenance of renal perfusion. In these patients administration of an NSAID may cause a dose-dependent reduction in prostaglandin formation and, secondarily, in renal blood flow, which may precipitate overt renal decompensation. Patients at greatest risk of this reaction are those with impaired renal function, dehydration, hypovolemia, heart failure, liver dysfunction, salt depletion, those taking diuretics and angiotensin-converting enzyme (ACE) inhibitors or ARBs, and the elderly. Discontinuation of NSAID therapy is usually followed by recovery to the pretreatment state.

TREXIMET should be discontinued if clinical signs and symptoms consistent with renal disease develop or if systemic manifestations occur.

TREXIMET is not recommended for use in patients with severe renal impairment (creatinine clearance [CrCl] <30 mL/min) unless the benefits are expected to outweigh the risk of worsening renal function [see Use in Specific Populations (8.6), Clinical Pharmacology (12.3)]. If TREXIMET is used in patients with advanced renal disease, monitor patients for signs of worsening renal function. Monitor renal function in patients with mild (CrCl = 60 to 89 mL/min) or moderate (CrCl = 30 to 59 mL/min) renal impairment, preexisting kidney disease, or dehydration.

The renal effects of TREXIMET may hasten the progression of renal dysfunction in patients with pre-existing renal disease.

Correct volume status in dehydrated or hypovolemic patients prior to initiating TREXIMET. Monitor renal function in patients with renal or hepatic impairment, heart failure, dehydration, or hypovolemia during use of TREXIMET [see Drug Interactions (7)]. Avoid the use of TREXIMET in patients with advanced renal disease unless the benefits are expected to outweigh the risk of worsening renal function. If TREXIMET is used in patients with advanced renal disease, monitor patients for signs of worsening renal function.

Hyperkalemia

Increases in serum potassium concentration, including hyperkalemia, have been reported with the use of NSAIDs, even in some patients without renal impairment. In patients with normal renal function, these effects have been attributed to a hyporeninemic-hypoaldosteronism state.

5.13 Anaphylactic Reactions

Anaphylactic reactions may occur in patients without known prior exposure to either component of TREXIMET. Such reactions can be life-threatening or fatal. In general, anaphylactic reactions to drugs are more likely to occur in individuals with a history of sensitivity to multiple allergens although anaphylactic reactions with naproxen have occurred in patient without known hypersensitivity to naproxen or to patients with aspirin sensitive asthma [see Contraindications (4) and Warnings and Precautions (5.18)]. TREXIMET should not be given to patients with the aspirin triad. This symptom complex typically occurs in patients with asthma who experience rhinitis with or without nasal polyps, or who exhibit severe, potentially fatal bronchospasm after taking aspirin or other NSAIDs [see Contraindications (4)].

TREXIMET is contraindicated in patients with a history of hypersensitivity reaction to sumatriptan, naproxen, or any other component of TREXIMET. Naproxen has been associated with anaphylactic reactions in patients without known hypersensitivity to naproxen and in patients with aspirin-sensitive asthma [see Contraindications (4) and Warnings and Precautions (5.18)]. Seek emergency help if an anaphylactic reaction occurs.

5.14 Serious Skin Reactions

NSAID-containing products can cause serious skin adverse reactions such as exfoliative dermatitis, Stevens-Johnson syndrome (SJS), and toxic epidermal necrolysis (TEN), which can be fatal. NSAIDs can also cause fixed drug eruption (FDE). FDE may present as a more severe variant known as generalized bullous fixed drug eruption (GBFDE), which can be life-threatening. These serious events may occur without warning. Inform patients about the signs and symptoms of serious skin reactions and to discontinue the use of TREXIMET at the first appearance of skin rash or any other sign of hypersensitivity. TREXIMET is contraindicated in patients with previous serious skin reactions to NSAIDs [see Contraindications (4)].

5.15 Drug Reaction with Eosinophilia and Systemic Symptoms (DRESS)

Drug Reaction with Eosinophilia and Systemic Symptoms (DRESS) has been reported in patients taking NSAIDs such as TREXIMET. Some of these events have been fatal or life-threatening. DRESS typically, although not exclusively, presents with fever, rash, lymphadenopathy, and/or facial swelling. Other clinical manifestations may include hepatitis, nephritis, hematological abnormalities, myocarditis, or myositis. Sometimes symptoms of DRESS may resemble an acute viral infection. Eosinophilia is often present. Because this disorder is variable in its presentation, other organ systems not noted here may be involved. It is important to note that early manifestations of hypersensitivity, such as fever or lymphadenopathy, may be present even though rash is not evident. If such signs or symptoms are present, discontinue TREXIMET and evaluate the patient immediately.

5.16 Fetal Toxicity

Premature Closure of Fetal Ductus Arteriosus

Avoid use of NSAIDs, including TREXIMET, in pregnant women at about 30 weeks gestation and later. NSAIDs, including TREXIMET, increase the risk of premature closure of the fetal ductus arteriosus at approximately this gestational age.

Oligohydramnios/Neonatal Renal Impairment

Use of NSAIDs, including TREXIMET, at about 20 weeks gestation or later in pregnancy may cause fetal renal dysfunction leading to oligohydramnios and, in some cases, neonatal renal impairment. These adverse outcomes are seen, on average, after days to weeks of treatment, although oligohydramnios has been infrequently reported as soon as 48 hours after NSAID initiation. Oligohydramnios is often, but not always, reversible with treatment discontinuation. Complications of prolonged oligohydramnios may, for example, include limb contractures and delayed lung maturation. In some postmarketing cases of impaired neonatal renal function, invasive procedures such as exchange transfusion or dialysis were required.

If NSAID treatment is necessary between about 20 weeks and 30 weeks gestation, limit TREXIMET use to the lowest effective dose and shortest duration possible. Consider ultrasound monitoring of amniotic fluid if TREXIMET treatment extends beyond 48 hours. Discontinue TREXIMET if oligohydramnios occurs and follow up according to clinical practice [see Use in Specific Populations (8.1)].

5.17 Hematologic Toxicity

Anemia has occurred in patients receiving NSAIDs. This may be due to fluid retention, occult or gross gastrointestinal blood loss, or an incompletely described effect upon erythropoiesis. If a patient treated with TREXIMET has signs or symptoms of anemia, monitor hemoglobin or hematocrit.

NSAIDs, including TREXIMET, may increase the risk of bleeding events. Co-morbid conditions such as coagulation disorders or concomitant use of warfarin, other anticoagulants, antiplatelet agents (e.g., aspirin), serotonin reuptake inhibitors (SSRIs), and serotonin norepinephrine reuptake inhibitors (SNRIs) may increase this risk. Monitor these patients for signs of bleeding [see Drug Interactions (7)].

5.18 Exacerbation of Asthma Related to Aspirin Sensitivity

A subpopulation of patients with asthma may have aspirin-sensitive asthma which may include chronic rhinosinusitis complicated by nasal polyps; severe, potentially fatal bronchospasm; and/or intolerance to aspirin and other NSAIDs. Because cross-reactivity between aspirin and other NSAIDs has been reported in such aspirin-sensitive patients, TREXIMET is contraindicated in patients with this form of aspirin sensitivity and should be used with caution in patients with preexisting asthma [see Contraindications (4)].

When TREXIMET is used in patients with preexisting asthma (without known aspirin sensitivity), monitor patients for changes in the signs and symptoms of asthma.

5.19 Seizures

Seizures have been reported following administration of sumatriptan. Some have occurred in patients with either a history of seizures or concurrent conditions predisposing to seizures. There are also reports in patients where no such predisposing factors are apparent. TREXIMET should be used with caution in patients with a history of epilepsy or conditions associated with a lowered seizure threshold.

5.20 Masking of Inflammation and Fever

The pharmacological activity of TREXIMET in reducing inflammation, and possibly fever, may diminish the utility of diagnostic signs in detecting infections.

5.21 Laboratory Monitoring

Because serious GI bleeding, hepatotoxicity, and renal injury can occur without warning symptoms or signs, consider monitoring patients on long-term NSAID treatment with a CBC and a chemistry profile periodically [see Warnings and Precautions (5.2, 5.7, 5.12)].

6 ADVERSE REACTIONS

The following serious adverse reactions are described below and elsewhere in labeling:

- Cardiovascular Thrombotic Events [see Warnings and Precautions (5.1)]
- GI Bleeding, Ulceration and Perforation [see Warnings and Precautions (5.2)]
- Arrhythmias [see Warnings and Precautions (5.3)]
- Chest, Throat, Neck, and/or Jaw Pain/Tightness/Pressure [see Warnings and Precautions (5.4)]
- Cerebrovascular Events [see Warnings and Precautions (5.5)]
- Other Vasospasm Reactions [see Warnings and Precautions (5.6)]
- Hepatotoxicity [see Warnings and Precautions (5.7)]
- Hypertension [see Warnings and Precautions (5.8)]
- Heart Failure and Edema [see Warnings and Precautions (5.9)]
- Medication Overuse Headache [see Warnings and Precautions (5.10)]
- Serotonin Syndrome [see Warnings and Precautions (5.11)]
- Renal Toxicity and Hyperkalemia [see Warnings and Precautions (5.12)]
- Anaphylactic Reactions [see Warnings and Precautions (5.13)]
- Serious Skin Reactions [see Warnings and Precautions (5.14)]
- Drug Reaction with Eosinophilia and Systemic Symptoms (DRESS) [see Warnings and Precautions (5.15)]
- Hematological Toxicity [see Warnings and Precautions (5.17)]
- Exacerbation Asthma Related to Aspirin Sensitivity [see Warnings and Precautions (5.18)]
- Seizures [see Warnings and Precautions (5.19)]

6.1 Clinical Trials Experience

Because clinical trials are conducted under widely varying conditions, adverse reaction rates observed in the clinical trials of a drug cannot be directly compared with rates in the clinical trials of another drug and may not reflect the rates observed in practice.

Adults

The adverse reactions reported below are specific to the clinical trials with TREXIMET 85/500 mg. See also the full prescribing information for naproxen and sumatriptan products.

Table 1 lists adverse reactions that occurred in 2 placebo-controlled clinical trials (Study 1 and 2) in adult patients who received 1 dose of study drug. Only adverse reactions that occurred at a frequency of 2% or more in any group treated with TREXIMET 85/500 mg and that occurred at a frequency greater than the placebo group are included in Table 1.

Table 1. Adverse Reactions in Pooled Placebo-Controlled Trials in Adult Patients with Migraine
Adverse Reactions | TREXIMET 85/500 mg % (n = 737) | Placebo % (n = 752) | Sumatriptan 85 mg % (n = 735) | Naproxen Sodium 500 mg % (n = 732)
Nervous system disorders
Dizziness | 4 | 2 | 2 | 2
Somnolence | 3 | 2 | 2 | 2
Paresthesia | 2 | <1 | 2 | <1
Gastrointestinal disorders
Nausea | 3 | 1 | 3 | <1
Dyspepsia | 2 | 1 | 2 | 1
Dry mouth | 2 | 1 | 2 | <1
Pain and other pressure sensations
Chest discomfort/chest pain | 3 | <1 | 2 | 1
Neck/throat/jaw pain/tightness/pressure | 3 | 1 | 3 | 1

The incidence of adverse reactions in controlled clinical trials was not affected by gender or age of the patients. There were insufficient data to assess the impact of race on the incidence of adverse reactions.

Pediatric Patients 12 to 17 Years of Age

In a placebo controlled clinical trial that evaluated pediatric patients 12 to 17 years of age who received 1 dose of TREXIMET 10/60 mg, 30/180 mg, or 85/500 mg, adverse reactions occurred in 13% of patients who received 10/60 mg, 9% of patients who received 30/180 mg, 13% who received 85/500 mg, and 8% who received placebo. No patients who received TREXIMET experienced adverse reactions leading to withdrawal from the trial. The incidence of adverse reactions in pediatric patients 12 to 17 years of age was comparable across all 3 doses compared with placebo. Table 2 lists adverse reactions that occurred in a placebo-controlled trial in pediatric patients 12 to 17 years of age at a frequency of 2% or more with TREXIMET and were more frequent than the placebo group.

Table 2. Adverse Reactions in a Placebo-Controlled Trial in Pediatric Patients 12 to 17 Years of Age with Migraine
 | TREXIMET 10/60 mg % | TREXIMET 30/180 mg % | TREXIMET 85/500 mg % | Placebo %
Adverse Reactions | (n = 96) | (n = 97) | (n = 152) | (n = 145)
Vascular
Hot flush (i.e., hot flash[es]) | 0 | 2 | <1 | 0
Musculoskeletal
Muscle tightness | 0 | 0 | 2 | 0

6.2 Postmarketing Experience

The following adverse reactions have been identified during post-approval use of NSAIDs, such as naproxen, which is a component of TREXIMET. Because these reactions are reported voluntarily from a population of uncertain size, it is not always possible to reliably estimate their frequency or establish a causal relationship to drug exposure.

Skin and Appendages: exfoliative dermatitis, Stevens-Johnson Syndrome (SJS), toxic epidermal necrolysis (TEN), and fixed drug eruption (FDE) [see Warnings and Precautions (5.14)].

7 DRUG INTERACTIONS

7.1 Clinically Significant Drug Interactions with TREXIMET

See Table 3 for clinically significant drug interactions with NSAIDs or Sumatriptan.

Table 3. Clinically Significant Drug Interactions with Naproxen or Sumatriptan
Ergot-Containing Drugs
Clinical Impact: | Ergot-containing drugs have been reported to cause prolonged vasospastic reactions.
Intervention: | Because these effects may be additive, coadministration of TREXIMET and ergotamine-containing or ergot-type medications (like dihydroergotamine or methysergide) within 24 hours of each other is contraindicated.
Monoamine Oxidase-A Inhibitors
Clinical Impact: | MAO-A inhibitors increase systemic exposure of orally administered sumatriptan by 7-fold.
Intervention: | The use of TREXIMET in patients receiving MAO-A inhibitors is contraindicated.
Other 5-HT1 Agonists
Clinical Impact: | 5-HT1 agonist drugs can cause vasospastic effects.
Intervention: | Because these effects may be additive, coadministration of TREXIMET and other 5 HT1 agonists (e.g., triptans) within 24 hours of each other is contraindicated.
Drugs That Interfere with Hemostasis
Clinical Impact: | - Naproxen and anticoagulants such as warfarin have a synergistic effect on bleeding. The concomitant use of naproxen and anticoagulants have an increased risk of serious bleeding compared to the use of either drug alone. - Serotonin release by platelets plays an important role in hemostasis. Case-control and cohort epidemiological studies showed that concomitant use of drugs that interfere with serotonin reuptake and an NSAID may potentiate the risk of bleeding more than an NSAID alone.
Intervention: | Monitor patients with concomitant use of TREXIMET with anticoagulants (e.g., warfarin), antiplatelet agents (e.g., aspirin), selective serotonin reuptake inhibitors (SSRIs), and serotonin norepinephrine reuptake inhibitors (SNRIs) for signs of bleeding [see Warnings and Precautions (5.17)].
Aspirin
Clinical Impact: | A pharmacodynamic (PD) study has demonstrated an interaction in which lower dose naproxen (220mg/day or 220mg twice daily) interfered with the antiplatelet effect of low-dose immediate-release aspirin, with the interaction most marked during the washout period of naproxen [see Clinical Pharmacology (12.2)]. There is reason to expect that the interaction would be present with prescription doses of naproxen or with enteric-coated low-dose aspirin; however, the peak interference with aspirin function may be later than observed in the PD study due to the longer washout period. Controlled clinical studies showed that the concomitant use of NSAIDs and analgesic doses of aspirin does not produce any greater therapeutic effect than the use of NSAIDs alone. In a clinical study, the concomitant use of an NSAID and aspirin was associated with a significantly increased incidence of GI adverse reactions as compared to use of the NSAID alone [see Warnings and Precautions (5.2) and Clinical Pharmacology (12.3)].
Intervention: | Because there may be an increased risk of cardiovascular events following discontinuation of naproxen due to the interference with the antiplatelet effect of aspirin during the washout period, for patients taking low-dose aspirin for cardioprotection who require intermittent analgesics, consider use of an NSAID that does not interfere with the antiplatelet effect of aspirin, or non-NSAID analgesics where appropriate. Concomitant use of TREXIMET and analgesic doses of aspirin is not generally recommended because of the increased risk of bleeding [see Warnings and Precautions (5.17)].
Selective Serotonin Reuptake Inhibitors/Serotonin Norepinephrine Reuptake Inhibitors and Serotonin Syndrome
Clinical Impact: | Cases of serotonin syndrome have been reported during coadministration of triptans and SSRIs, SNRIs, TCAs, and MAO inhibitors [see Warnings and Precautions (5.11)].
Intervention: | Discontinue TREXIMET if serotonin syndrome is suspected.
ACE Inhibitors, Angiotensin Receptor Blockers, and Beta-blockers
Clinical Impact: | - NSAIDs may diminish the antihypertensive effect of angiotensin converting enzyme (ACE) inhibitors, angiotensin receptor blockers (ARBs), or beta-blockers (including propranolol). - In patients who are elderly, volume-depleted (including those on diuretic therapy), or have renal impairment, co-administration of an NSAID with ACE inhibitors or ARBs may result in deterioration of renal function, including possible acute renal failure. These effects are usually reversible.
Intervention: | - During concomitant use of TREXIMET and ACE-inhibitors, ARBs, or beta-blockers, monitor blood pressure to ensure that the desired blood pressure is obtained [see Warnings and Precautions (5.8)]. - During concomitant use of TREXIMET and ACE-inhibitors or ARBs in patients who are elderly, volume-depleted, or have impaired renal function, monitor for signs of worsening renal function [see Warnings and Precautions (5.8)].
Diuretics
Clinical Impact: | Clinical studies, as well as post-marketing observations, showed that NSAIDs reduced the natriuretic effect of loop diuretics (e.g., furosemide) and thiazide diuretics in some patients. This effect has been attributed to the NSAID inhibition of renal prostaglandin synthesis.
Intervention: | During concomitant use of TREXIMET with diuretics, observe patients for signs of worsening renal function, in addition to assuring diuretic efficacy including antihypertensive effects [see Warnings and Precautions (5.8, 5.12)].
Digoxin
Clinical Impact: | The concomitant use of naproxen with digoxin has been reported to increase the serum concentration and prolong the half-life of digoxin.
Intervention: | During concomitant use of TREXIMET and digoxin, monitor serum digoxin levels.
Lithium
Clinical Impact: | NSAIDs have produced elevations in plasma lithium levels and reductions in renal lithium clearance. The mean minimum lithium concentration increased 15%, and the renal clearance decreased by approximately 20%. This effect has been attributed to NSAID inhibition of renal prostaglandin synthesis.
Intervention: | During concomitant use of TREXIMET and lithium, monitor patients for signs of lithium toxicity.
Methotrexate
Clinical Impact: | Concomitant administration of some NSAIDs with high-dose methotrexate therapy has been reported to elevate and prolong serum methotrexate levels, resulting in deaths from severe hematologic and gastrointestinal toxicity. Concomitant use of NSAIDs and methotrexate may increase the risk for methotrexate toxicity (e.g., neutropenia, thrombocytopenia, renal dysfunction).
Intervention: | During concomitant use of TREXIMET and methotrexate, monitor patients for methotrexate toxicity.
Cyclosporine
Clinical Impact: | Concomitant use of NSAIDs and cyclosporine may increase cyclosporine's nephrotoxicity.
Intervention: | During concomitant use of TREXIMET and cyclosporine, monitor patients for signs of worsening renal function.
NSAIDs and Salicylates
Clinical Impact: | Concomitant use of naproxen with other NSAIDs or salicylates (e.g., diflunisal, salsalate) increases the risk of GI toxicity, with little or no increase in efficacy [see Warnings and Precautions (5.2)].
Intervention: | The concomitant use of naproxen with other NSAIDs or salicylates is not recommended.
Pemetrexed
Clinical Impact: | Concomitant use of NSAIDs and pemetrexed may increase the risk of pemetrexed-associated myelosuppression, renal, and GI toxicity (see the pemetrexed prescribing information).
Intervention: | During concomitant use of TREXIMET and pemetrexed, in patients with renal impairment whose creatinine clearance ranges from 45 to 79 mL/min, monitor for myelosuppression, renal and GI toxicity. NSAIDs with short elimination half-lives (e.g., diclofenac, indomethacin) should be avoided for a period of two days before, the day of, and two days following administration of pemetrexed. In the absence of data regarding potential interaction between pemetrexed and NSAIDs with longer half-lives (e.g., meloxicam, nabumetone), patients taking these NSAIDs should interrupt dosing for at least five days before, the day of, and two days following pemetrexed administration.
Probenecid
Clinical Impact: | Probenecid given concurrently increases naproxen anion plasma levels and extends its plasma half-life significantly. The clinical significance of this is unknown.
Intervention: | Reduce the frequency of administration of Treximet when given concurrently with probenecid.

7.2 Drug/Laboratory Test Interactions

Blood Tests

Naproxen may decrease platelet aggregation and prolong bleeding time. This effect should be kept in mind when bleeding times are determined.

Urine Tests

The administration of naproxen sodium may result in increased urinary values for 17-ketogenic steroids because of an interaction between the drug and/or its metabolites with m-di-nitrobenzene used in this assay. Although 17-hydroxy-corticosteroid measurements (Porter-Silber test) do not appear to be artificially altered, it is suggested that therapy with naproxen be temporarily discontinued 72 hours before adrenal function tests are performed if the Porter-Silber test is to be used.

Naproxen may interfere with some urinary assays of 5-hydroxy indoleacetic acid (5HIAA).

8 USE IN SPECIFIC POPULATIONS

8.1 Pregnancy

Risk Summary

Use of NSAIDs, including TREXIMET, can cause premature closure of the fetal ductus arteriosus and fetal renal dysfunction leading to oligohydramnios and, in some cases, neonatal renal impairment. Because of these risks, limit dose and duration of TREXIMET use between about 20 and 30 weeks of gestation, and avoid TREXIMET use at about 30 weeks of gestation and later in pregnancy (see Clinical Considerations, Data).

Premature Closure of Fetal Ductus Arteriosus

Use of NSAIDs, including TREXIMET, at about 30 weeks gestation or later in pregnancy increases the risk of premature closure of the fetal ductus arteriosus.

Oligohydramnios/Neonatal Renal Impairment

Use of NSAIDs at about 20 weeks gestation or later in pregnancy has been associated with cases of fetal renal dysfunction leading to oligohydramnios, and in some cases, neonatal renal impairment.

Data from observational studies regarding other potential embryofetal risks of NSAID use in women in the first or second trimesters of pregnancy are inconclusive.

Data from a prospective pregnancy exposure registry and epidemiological studies of pregnant women have not detected an increased frequency of birth defects or a consistent pattern of birth defects among women exposed to sumatriptan compared with the general population (see Human Data). In animal studies, administration of sumatriptan and naproxen, alone or in combination, during pregnancy resulted in developmental toxicity (increased incidences of fetal malformations, embryofetal and pup mortality, decreased embryofetal growth) at clinically relevant doses (see Animal Data). Based on animal data, prostaglandins have been shown to have an important role in endometrial vascular permeability, blastocyst implantation, and decidualization. In animal studies, administration of prostaglandin synthesis inhibitors such as naproxen sodium resulted in increased pre- and post-implantation loss. Prostaglandins also have been shown to have an important role in fetal kidney development. In published animal studies, prostaglandin synthesis inhibitors have been reported to impair kidney development when administered at clinically relevant doses.

All pregnancies have a background risk of birth defects, loss, or other adverse outcomes. In the U.S. general population, the estimated background risk of major birth defects and miscarriage in clinically recognized pregnancies is 2-4% and 15-20%, respectively. The reported rate of major birth defects among deliveries to women with migraine ranged from 2.2% to 2.9% and the reported rate of miscarriage was 17%, which were similar to rates reported in women without migraine.

Clinical Considerations

Disease-Associated Maternal and/or Embryo/Fetal Risk

Several studies have suggested that women with migraine may be at increased risk of preeclampsia and gestational hypertension during pregnancy.

Fetal/Neonatal Adverse Reactions

Premature Closure of Fetal Ductus Arteriosus:

Avoid use of NSAIDs in women at about 30 weeks gestation and later in pregnancy, because NSAIDs, including TREXIMET, can cause premature closure of the fetal ductus arteriosus (see Data).

Oligohydramnios/Neonatal Renal Impairment:

If an NSAID is necessary at about 20 weeks gestation or later in pregnancy, limit the use to the lowest effective dose and shortest duration possible. If TREXIMET treatment extends beyond 48 hours, consider monitoring with ultrasound for oligohydramnios. If oligohydramnios occurs, discontinue TREXIMET and follow up according to clinical practice (see Data).

Labor or Delivery

There are no studies on the effects of naproxen tablets during labor or delivery. In animal studies, NSAIDS, including naproxen, inhibit prostaglandin synthesis, cause delayed parturition, and increase the incidence of stillbirth.

Data

Human Data

There is some evidence to suggest that when inhibitors of prostaglandin synthesis are used to delay preterm labor, there is an increased risk of neonatal complications such as necrotizing enterocolitis, patent ductus arteriosus, and intracranial hemorrhage. Naproxen treatment given in late pregnancy to delay parturition has been associated with persistent pulmonary hypertension, renal dysfunction, and abnormal prostaglandin E levels in preterm infants.

The Sumatriptan/Naratriptan/Treximet (sumatriptan and naproxen sodium) Pregnancy Registry, a population-based international prospective study, collected data for sumatriptan from January 1996 to September 2012. The Registry included only 6 pregnancy exposures to TREXIMET, with no major birth defects reported. The Registry documented outcomes of 626 infants and fetuses exposed to sumatriptan during pregnancy (528 with earliest exposure during the first trimester, 78 during the second trimester, 16 during the third trimester, and 4 unknown). The occurrence of major birth defects (excluding fetal deaths and induced abortions without reported defects and all spontaneous pregnancy losses) during first-trimester exposure to sumatriptan was 4.2% (20/478 [95% CI: 2.6% to 6.5%]) and during any trimester of exposure was 4.2% (24/576 [95% CI: 2.7% to 6.2%]). The sample size in this study had 80% power to detect at least a 1.73- to 1.91-fold increase in the rate of major malformations. The number of exposed pregnancy outcomes accumulated during the registry was insufficient to support definitive conclusions about overall malformation risk or to support making comparisons of the frequencies of specific birth defects. Of the 20 infants with reported birth defects after exposure to sumatriptan in the first trimester, 4 infants had ventricular septal defects, including one infant who was exposed to both sumatriptan and naratriptan, and 3 infants had pyloric stenosis. No other birth defect was reported for more than 2 infants in this group.

In a study using data from the Swedish Medical Birth Register, live births to women who reported using triptans or ergots during pregnancy were compared with those of women who did not. Of the 2,257 births with first-trimester exposure to sumatriptan, 107 infants were born with malformations (relative risk 0.99 [95% CI: 0.91 to 1.21]). A study using linked data from the Medical Birth Registry of Norway to the Norwegian Prescription Database compared pregnancy outcomes in women who redeemed prescriptions for triptans during pregnancy, as well as a migraine disease comparison group who redeemed prescriptions for sumatriptan before pregnancy only, compared with a population control group. Of the 415 women who redeemed prescriptions for sumatriptan during the first trimester, 15 had infants with major congenital malformations (OR 1.16 [95% CI: 0.69 to 1.94]) while for the 364 women who redeemed prescriptions for sumatriptan before, but not during, pregnancy, 20 had infants with major congenital malformations (OR 1.83 [95% CI: 1.17 to 2.88]), each compared with the population comparison group. Additional smaller observational studies evaluating use of sumatriptan during pregnancy have not suggested an increased risk of teratogenicity.

Premature Closure of Fetal Ductus Arteriosus:

Published literature reports that the use of NSAIDs at about 30 weeks of gestation and later in pregnancy may cause premature closure of the fetal ductus arteriosus.

Oligohydramnios/Neonatal Renal Impairment:

Published studies and postmarketing reports describe maternal NSAID use at about 20 weeks gestation or later in pregnancy associated with fetal renal dysfunction leading to oligohydramnios, and in some cases, neonatal renal impairment. These adverse outcomes are seen, on average, after days to weeks of treatment, although oligohydramnios has been infrequently reported as soon as 48 hours after NSAID initiation. In many cases, but not all, the decrease in amniotic fluid was transient and reversible with cessation of the drug. There have been a limited number of case reports of maternal NSAID use and neonatal renal dysfunction without oligohydramnios, some of which were irreversible. Some cases of neonatal renal dysfunction required treatment with invasive procedures, such as exchange transfusion or dialysis.

Methodological limitations of these postmarketing studies and reports include lack of a control group; limited information regarding dose, duration, and timing of drug exposure; and concomitant use of other medications. These limitations preclude establishing a reliable estimate of the risk of adverse fetal and neonatal outcomes with maternal NSAID use. Because the published safety data on neonatal outcomes involved mostly preterm infants, the generalizability of certain reported risks to the full-term infant exposed to NSAIDs through maternal use is uncertain.

Animal Data

Oral administration of sumatriptan alone to pregnant rats during the period of organogenesis resulted in an increased incidence of fetal blood vessel (cervicothoracic and umbilical) abnormalities. The highest no-effect dose for embryofetal developmental toxicity in rats was 60 mg/kg/day, or approximately 3 times the maximum recommended human dose (MRHD) of 170 mg/day on a mg/m^2 basis.

Oral administration of sumatriptan alone to pregnant rabbits during the period of organogenesis resulted in increased incidences of embryolethality and fetal cervicothoracic vascular and skeletal abnormalities. Intravenous administration of sumatriptan to pregnant rabbits during the period of organogenesis resulted in an increased incidence of embryolethality. The highest oral and intravenous no-effect doses for developmental toxicity in rabbits were 15 (approximately 2 times the MRHD on a mg/m^2 basis) and 0.75 mg/kg/day, respectively.

Oral administration of sumatriptan combined with naproxen sodium (5/9, 25/45, or 50/90 mg/kg/day sumatriptan/naproxen sodium) or each drug alone (50/0, 0/90 mg/kg/day sumatriptan/naproxen sodium) to pregnant rabbits during the period of organogenesis resulted in increased total incidences of fetal abnormalities at all doses and increased incidences of specific malformations (cardiac interventricular septal defect in the 50/90 mg/kg/day group, fused caudal vertebrae in the 50/0 and 0/90 mg/kg/day groups) and variations (absent intermediate lobe of the lung, irregular ossification of the skull, incompletely ossified sternal centra) at the highest dose of sumatriptan and naproxen alone and in combination. A no-effect dose for developmental toxicity in rabbit was not established. The lowest effect dose of 5/9 mg/kg/day sumatriptan/naproxen sodium was associated with plasma exposures (AUC) to sumatriptan and naproxen that were less than those attained at the MRHD of 170 mg sumatriptan and 1000 mg naproxen sodium (two tablets of TREXIMET 85/500 mg in a 24-hour period).

Oral administration of sumatriptan alone to rats prior to and throughout gestation resulted in embryofetal toxicity (decreased body weight, decreased ossification, increased incidence of skeletal abnormalities). The highest no-effect dose was 50 mg/kg/day, or approximately 3 times the MRHD on a mg/m^2 basis. In offspring of pregnant rats treated orally with sumatriptan during organogenesis, there was a decrease in pup survival. The highest no-effect dose for this effect was 60 mg/kg/day, or approximately 3 times the MRHD on a mg/m^2 basis. Oral treatment of pregnant rats with sumatriptan during the latter part of gestation and throughout lactation resulted in a decrease in pup survival. The highest no-effect dose for this finding was 100 mg/kg/day, or approximately 6 times the MRHD on a mg/m^2 basis.

In reproduction studies of naproxen in rats (20 mg/kg/day), rabbits (20 mg/kg/day, and mice (170 mg/kg/day, no evidence of impaired fertility or harm to the fetus was observed. The doses tested in rats, rabbits, and mice were less (≤0.8 times) the MRHD, based on body surface area (mg/m^2) comparisons.

8.2 Lactation

Risk Summary

The naproxen anion has been found in the milk of lactating women at a concentration equivalent to approximately 1% of maximum naproxen concentration in plasma. Sumatriptan is excreted in human milk following subcutaneous administration (see Data). There is no information regarding sumatriptan concentrations in milk from lactating women following administration of sumatriptan tablets.

There are no data on the effects of naproxen or sumatriptan on the breastfed infant or the effects of naproxen or sumatriptan on milk production.

The developmental and health benefits of breastfeeding should be considered along with the mother's clinical need for TREXIMET and any potential adverse effects on the breastfed infant from TREXIMET or from the underlying maternal condition.

Clinical Considerations

Infant exposure to sumatriptan can be minimized by avoiding breastfeeding for 12 hours after treatment with sumatriptan tablets.

Data

Following subcutaneous administration of a 6-mg dose of sumatriptan injection in 5 lactating volunteers, sumatriptan was present in milk.

8.3 Females and Males of Reproductive Potential

Infertility

Females

Based on the mechanism of action, the use of prostaglandin-mediated NSAIDs, including naproxen tablets, may delay or prevent rupture of ovarian follicles, which has been associated with reversible infertility in some women. Published animal studies have shown that administration of prostaglandin synthesis inhibitors has the potential to disrupt prostaglandin-mediated follicular rupture required for ovulation. Small studies in women treated with NSAIDs have also shown a reversible delay in ovulation. Consider withdrawal of NSAIDs, including naproxen tablets, in women who have difficulties conceiving or who are undergoing investigation of infertility.

8.4 Pediatric Use

Safety and effectiveness of TREXIMET in pediatric patients under 12 years of age have not been established.

The safety and efficacy of TREXIMET for the acute treatment of migraine in pediatric patients 12 to 17 years of age was established in a double-blind, placebo-controlled trial [see Adverse Reactions (6.1) and Clinical Studies (14.2)].

8.5 Geriatric Use

Elderly patients, compared to younger patients, are at greater risk for NSAID-associated serious cardiovascular, gastrointestinal, and/or renal adverse reactions. TREXIMET is not recommended for use in elderly patients who have decreased renal function, higher risk for unrecognized CAD, and increases in blood pressure that may be more pronounced in the elderly [see Warnings and Precautions (5.1, 5.2, 5.3, 5.8, 5.12) and Clinical Pharmacology (12.3)].

A cardiovascular evaluation is recommended for geriatric patients who have other cardiovascular risk factors (e.g., diabetes, hypertension, smoking, obesity, strong family history of CAD) prior to receiving TREXIMET [see Warnings and Precautions (5.1)].

8.6 Renal Impairment

TREXIMET is not recommended for use in patients with creatinine clearance less than 30 mL/min. Monitor the serum creatinine or creatinine clearance in patients with mild (CrCl = 60 to 89 mL/min) or moderate (CrCL = 30 to 59 mL/min) renal impairment, preexisting kidney disease, or dehydration [see Warnings and Precautions (5.12) and Clinical Pharmacology (12.3)].

8.7 Hepatic Impairment

TREXIMET is contraindicated in patients with severe hepatic impairment. For patients with mild or moderate hepatic impairment, the TREXIMET dose should be reduced. [see Contraindications (4), Warnings and Precautions (5.7), and Clinical Pharmacology (12.3)].

10 OVERDOSAGE

Patients (N = 670) have received single oral doses of 140 to 300 mg of sumatriptan without significant adverse effects. Volunteers (N = 174) have received single oral doses of 140 to 400 mg without serious adverse events.

Overdose of sumatriptan in animals has been fatal and has been heralded by convulsions, tremor, paralysis, inactivity, ptosis, erythema of the extremities, abnormal respiration, cyanosis, ataxia, mydriasis, salivation, and lacrimation.

Symptoms following acute NSAID overdosages have been typically limited to lethargy, drowsiness, nausea, vomiting and epigastric pain. Gastrointestinal bleeding has occurred. Hypertension, acute renal failure, respiratory depression, and coma have occurred, but were rare [see Warnings and Precautions (5.1, 5.2)].

Manage patients with symptomatic and supportive care following an NSAID overdosage. There are no specific antidotes. Consider emesis and/or activated charcoal (60 to 100 grams in adults, 1 to 2 grams per kg of body weight in pediatric patients) and/or osmotic cathartic in symptomatic patients seen within four hours of ingestion or in patients with a large overdosage (5 to 10 times the recommended dosage). Hemodialysis does not decrease the plasma concentration of naproxen because of the high degree of its protein binding. It is unknown what effect hemodialysis or peritoneal dialysis has on the serum concentrations of sumatriptan. Forced diuresis, alkalinization of urine, hemodialysis, or hemoperfusion may not be useful due to high protein binding.

For additional information about overdosage treatment contact a poison control center (1-800-222-1222).

11 DESCRIPTION

TREXIMET contains sumatriptan (as the succinate), a selective 5-hydroxytryptamine1 (5-HT1) receptor subtype agonist, and naproxen sodium, a member of the arylacetic acid group of NSAIDs.

Sumatriptan succinate is chemically designated as 3-[2-(dimethylamino)ethyl]-N-methyl-indole-5-methanesulfonamide succinate (1:1), and it has the following structure:

The empirical formula is C14H21N3O2S∙C4H6O4, representing a molecular weight of 413.5. Sumatriptan succinate is a white to off-white powder that is readily soluble in water and in saline.

Naproxen sodium is chemically designated as (S)-6-methoxy-α-methyl-2-naphthaleneacetic acid, sodium salt, and it has the following structure:

The empirical formula is C14H13NaO3, representing a molecular weight of 252.23. Naproxen sodium is a white-to-creamy white crystalline solid, freely soluble in water at neutral pH.

Each TREXIMET 85/500 mg tablet for oral administration contains 119 mg of sumatriptan succinate equivalent to 85 mg of sumatriptan and 500 mg of naproxen sodium. Each tablet also contains the inactive ingredients croscarmellose sodium, dibasic calcium phosphate, FD&C Blue No. 2, hypromellose, magnesium stearate, microcrystalline cellulose, povidone, sodium bicarbonate, talc, titanium dioxide, and triacetin.

Each TREXIMET 10/60 mg tablet for oral administration contains 14 mg of sumatriptan succinate equivalent to 10 mg of sumatriptan and 60 mg of naproxen sodium. Each tablet also contains the inactive ingredients croscarmellose sodium, dibasic calcium phosphate, FD&C Blue No. 2, magnesium stearate, microcrystalline cellulose, polyethylene glycol, polyvinyl alcohol, povidone, sodium bicarbonate, talc, and titanium dioxide.

12 CLINICAL PHARMACOLOGY

12.1 Mechanism of Action

TREXIMET contains sumatriptan and naproxen.

Sumatriptan binds with high affinity to cloned 5-HT1B/1D receptors. Sumatriptan presumably exerts its therapeutic effects in the treatment of migraine headache through agonist effects at the 5-HT1B/1D receptors on intracranial blood vessels and sensory nerves of the trigeminal system, which result in cranial vessel constriction and inhibition of neuropeptide release.

TREXIMET has analgesic, anti-inflammatory, and antipyretic properties. The mechanism of action of TREXIMET, like that of other NSAIDs, is not completely understood but involves inhibition of cyclooxygenase (COX-1 and COX-2).

Naproxen is a potent inhibitor of prostaglandin synthesis in vitro. Naproxen concentrations reached during therapy have produced in vivo effects. Prostaglandins sensitize afferent nerves and potentiate the action of bradykinin in inducing pain in animal models. Prostaglandins are mediators of inflammation. Because naproxen is an inhibitor of prostaglandin synthesis, its mode of action may be due to a decrease of prostaglandins in peripheral tissues.

12.2 Pharmacodynamics

In a healthy volunteer study, 10 days of concomitant administration of naproxen 220 mg once-daily with low-dose immediate-release aspirin (81 mg) showed an interaction with the antiplatelet activity of aspirin as measured by % serum thromboxane B2 inhibition at 24 hours following the day 10 dose [98.7% (aspirin alone) vs 93.1% (naproxen and aspirin)]. The interaction was observed even following discontinuation of naproxen on day 11 (while aspirin dose was continued) but normalized by day 13. In the same study, the interaction was greater when naproxen was administered 30 minutes prior to aspirin [98.7% vs 87.7%] and minimal when aspirin was administered 30 minutes prior to naproxen [98.7% vs 95.4%].

Following administration of naproxen 220 mg twice-daily with low-dose immediate–release aspirin (first naproxen dose given 30 minutes prior to aspirin), the interaction was minimal at 24 h following day 10 dose [98.7% vs 95.7%]. However, the interaction was more prominent after discontinuation of naproxen (washout) on day 11 [98.7% vs 84.3%] and did not normalize completely by day 13 [98.5% vs 90.7%] [see Drug Interactions (7.1)].

Blood Pressure

In a randomized, double-blind, parallel group, active control trial, TREXIMET 85/500 mg administered intermittently over 6 months did not increase blood pressure in a normotensive adult population (n = 122). However, significant elevation in blood pressure has been reported with 5-HT1 agonists and NSAIDs in patients with and without a history of hypertension.

12.3 Pharmacokinetics

Absorption and Bioavailability

Sumatriptan, when given as TREXIMET 85/500 mg, has a mean Cmax similar to that of sumatriptan succinate 100 mg tablets alone. The median Tmax of sumatriptan, when given as TREXIMET 85/500 mg, was 1 hour (range: 0.3 to 4.0 hours), which is slightly different compared with sumatriptan succinate 100 mg tablets (median Tmax of 1.5 hours). Naproxen, when given as TREXIMET 85/500 mg, has a Cmax which is approximately 36% lower than naproxen sodium 550 mg tablets and a median Tmax of 5 hours (range: 0.3 to 12 hours), which is approximately 4 hours later than from naproxen sodium tablets 550 mg. AUC values for sumatriptan and for naproxen are similar for TREXIMET 85/500 mg compared with sumatriptan succinate 100 mg tablets or naproxen sodium 550 mg tablets, respectively. In a crossover trial in 16 subjects, the pharmacokinetics of both components administered as TREXIMET 85/500 mg were similar during a migraine attack and during a migraine-free period.

Bioavailability of sumatriptan is approximately 15%, primarily due to presystemic (first-pass) metabolism and partly due to incomplete absorption.

Naproxen is absorbed from the gastrointestinal tract with an in vivo bioavailability of 95%.

Food had no significant effect on the bioavailability of sumatriptan or naproxen administered as TREXIMET, but slightly delayed the Tmax of sumatriptan by about 0.6 hour [see Dosage and Administration (2.3)].

Distribution

Plasma protein binding is 14% to 21%. The effect of sumatriptan on the protein binding of other drugs has not been evaluated. The volume of distribution of sumatriptan is 2.7 L/kg.

The volume of distribution of naproxen is 0.16 L/kg. At therapeutic levels naproxen is greater than 99% albumin bound. At doses of naproxen greater than 500 mg/day, there is a less-than-proportional increase in plasma levels due to an increase in clearance caused by saturation of plasma protein binding at higher doses (average trough Css = 36.5, 49.2, and 56.4 mg/L with 500-; 1,000-; and 1,500-mg daily doses of naproxen, respectively). However, the concentration of unbound naproxen continues to increase proportionally to dose.

Metabolism

In vitro studies with human microsomes suggest that sumatriptan is metabolized by monoamine oxidase (MAO), predominantly the A isoenzyme. No significant effect was seen with an MAO-B inhibitor.

Naproxen is extensively metabolized to 6-0-desmethyl naproxen, and both parent and metabolites do not induce metabolizing enzymes.

Elimination

The elimination half-life of sumatriptan is approximately 2 hours. Radiolabeled ^14C-sumatriptan administered orally is largely renally excreted (about 60%), with about 40% found in the feces. Most of a radiolabeled dose of sumatriptan excreted in the urine is the major metabolite indole acetic acid (IAA) or the IAA glucuronide, both of which are inactive. Three percent of the dose can be recovered as unchanged sumatriptan.

The clearance of naproxen is 0.13 mL/min/kg. Approximately 95% of the naproxen from any dose is excreted in the urine, primarily as naproxen (less than 1%), 6-0-desmethyl naproxen (less than 1%), or their conjugates (66% to 92%). The plasma half-life of the naproxen anion in humans is approximately 19 hours. The corresponding half-lives of both metabolites and conjugates of naproxen are shorter than 12 hours, and their rates of excretion have been found to coincide closely with the rate of naproxen disappearance from the plasma. In patients with renal failure, metabolites may accumulate.

Specific Populations

Geriatrics

The pharmacokinetics of TREXIMET in geriatric patients have not been studied. Elderly patients are more likely to have decreased hepatic function and decreased renal function [see Specific Populations (8.5)].

The pharmacokinetics of oral sumatriptan in the elderly (mean age: 72 years, 2 males and 4 females) and in patients with migraine (mean age: 38 years, 25 males and 155 females) were similar to that in healthy male subjects (mean age: 30 years).

Studies indicate that although total plasma concentration of naproxen is unchanged, the unbound plasma fraction, which represents <1% of the total concentration, increased in the elderly (range of unbound trough naproxen from 0.12% to 0.19% in elderly subjects versus 0.05% to 0.075% in younger subjects).

Pediatrics

A pharmacokinetic study compared 3 doses of TREXIMET in pediatric patients 12 to 17 years of age (n=24) with adults (n=26). The AUC and Cmax of sumatriptan were 50-60% higher following a single dose of TREXIMET 10/60 mg in pediatric patients 12 to 17 years of age (n=7) compared with adult subjects (n=8), and were 6-26% higher following a single dose of TREXIMET 30/180 mg or 85/500 mg in pediatrics than adults. Naproxen pharmacokinetic parameters were similar between pediatrics and adults.

Renal Impairment

The effect of renal impairment on the pharmacokinetics of TREXIMET has not been studied. Since naproxen and its metabolites and conjugates are primarily excreted by the kidney, the potential exists for naproxen metabolites to accumulate in the presence of renal insufficiency. Elimination of naproxen is decreased in patients with severe renal impairment [see Warnings and Precautions (5.12), Use in Specific Populations (8.6)].

Hepatic Impairment

The effect of hepatic impairment on the pharmacokinetics of TREXIMET has not been studied. In a study in patients with moderate hepatic impairment (n = 8) matched for sex, age, and weight with healthy subjects (n = 8), patients with hepatic impairment had an approximately 70% increase in AUC and Cmax of sumatriptan and a Tmax 40 minutes earlier compared to healthy subjects. The pharmacokinetics of sumatriptan in patients with severe hepatic impairment has not been studied.

Gender

In a pooled analysis of 5 pharmacokinetic trials, there was no effect of gender on the systemic exposure of TREXIMET.

Race

The effect of race on the pharmacokinetics of TREXIMET has not been studied. The systemic clearance and Cmax of sumatriptan were similar in black (n = 34) and white (n = 38) healthy male subjects.

Drug Interaction Studies

Aspirin

When naproxen was administered with aspirin (>1 gram/day), the protein binding of naproxen was reduced, although the clearance of free naproxen was not altered. See Table 3 for clinically significant drug interactions of naproxen, an NSAID, with aspirin [see Drug Interactions (7)].

Propranolol

Propranolol 80 mg given twice daily had no significant effect on sumatriptan pharmacokinetics. See Table 3 for clinically significant drug interactions of propranolol, a beta-blocker, with TREXIMET [see Drug Interactions (7)].

13 NONCLINICAL TOXICOLOGY

13.1 Carcinogenesis, Mutagenesis, Impairment of Fertility

Carcinogenesis

The carcinogenic potential of TREXIMET has not been studied.

In carcinogenicity studies in mouse and rat, sumatriptan was administered orally for 78 and 104 weeks, respectively, at doses up to 160 mg/kg/day. The highest doses tested are approximately 5 (mouse) and 9 (rat) times the maximum human daily dose (MHDD) of 170 mg sumatriptan on a mg/m^2 basis (two tablets of TREXIMET 85/500 mg in a 24-hour period).

The carcinogenic potential of naproxen was evaluated in a 2-year oral carcinogenicity study in rats at doses of 8, 16, and 24 mg/kg/day and in another 2-year oral carcinogenicity study in rats at a dose of 8 mg/kg/day. No evidence of tumorigenicity was found in either study. The highest dose tested is less than the MHDD (1000 mg) of naproxen, on a mg/m^2 basis.

Mutagenesis

Sumatriptan and naproxen sodium tested alone and in combination were negative in an in vitro bacterial reverse mutation assay, and in an in vivo micronucleus assay in mice.

The combination of sumatriptan and naproxen sodium was negative in an in vitro mouse lymphoma tk assay in the presence and absence of metabolic activation. However, in separate in vitro mouse lymphoma tk assays, naproxen sodium alone was reproducibly positive in the presence of metabolic activation.

Naproxen sodium alone and in combination with sumatriptan was positive in an in vitro clastogenicity assay in mammalian cells in the presence and absence of metabolic activation. The clastogenic effect for the combination was reproducible within this assay and was greater than observed with naproxen sodium alone. Sumatriptan alone was negative in these assays.

Chromosomal aberrations were not induced in peripheral blood lymphocytes following 7 days of twice-daily dosing with TREXIMET in human volunteers.

In previous studies, sumatriptan alone was negative in in vitro (bacterial reverse mutation [Ames], gene cell mutation in Chinese hamster V79/HGPRT, chromosomal aberration in human lymphocytes) and in vivo (rat micronucleus) assays.

Impairment of Fertility

The effect of TREXIMET on fertility in animals has not been studied.

When sumatriptan (5, 50, 500 mg/kg/day) was administered orally to male and female rats prior to and throughout the mating period, there was a drug-related decrease in fertility secondary to a decrease in mating in animals treated with doses greater than 5 mg/kg/day (less than the MHDD of 170 mg on a mg/m^2 basis). It is not clear whether this finding was due to an effect on males or females or both.

13.2 Animal Toxicology and/or Pharmacology

Corneal Opacities

Dogs receiving oral sumatriptan developed corneal opacities and defects in the corneal epithelium. Corneal opacities were seen at the lowest dosage tested, 2 mg/kg/day, and were present after 1 month of treatment. Defects in the corneal epithelium were noted in a 60-week study. Earlier examinations for these toxicities were not conducted and no-effect doses were not established. The lowest dose tested is less than the MHDD (170 mg) of sumatriptan on a mg/m^2 basis.

14 CLINICAL STUDIES

14.1 Adults

The efficacy of TREXIMET in the acute treatment of migraine with or without aura in adults was demonstrated in 2 randomized, double-blind, multicenter, parallel-group trials utilizing placebo and each individual active component of TREXIMET 85/500 mg (sumatriptan and naproxen sodium) as comparison treatments (Study 1 and Study 2). Patients enrolled in these 2 trials were predominately female (87%) and white (88%), with a mean age of 40 years (range: 18 to 65 years). Patients were instructed to treat a migraine of moderate to severe pain with 1 tablet. No rescue medication was allowed within 2 hours postdose. Patients evaluated their headache pain 2 hours after taking 1 dose of study medication; headache relief was defined as a reduction in headache severity from moderate or severe pain to mild or no pain. Associated symptoms of nausea, photophobia, and phonophobia were also evaluated. Sustained pain free was defined as a reduction in headache severity from moderate or severe pain to no pain at 2 hours postdose without a return of mild, moderate, or severe pain and no use of rescue medication for 24 hours postdose. The results from Study 1 and 2 are summarized in Table 4. In both trials, the percentage of patients achieving headache pain relief 2 hours after treatment was significantly greater among patients receiving TREXIMET 85/500 mg (65% and 57%) compared with those who received placebo (28% and 29%).

Further, the percentage of patients who remained pain free without use of other medications through 24 hours postdose was significantly greater among patients receiving a single dose of TREXIMET 85/500 mg (25% and 23%) compared with those who received placebo (8% and 7%) or either sumatriptan (16% and 14%) or naproxen sodium (10%) alone.

Table 4. Percentage of Adult Patients with 2-Hour Pain Relief and Sustained Pain Free Following Treatment [P values provided only for prespecified comparisons.]
 | TREXIMET 85/500 mg | Sumatriptan 85 mg | Naproxen Sodium 500 mg | Placebo
2-Hour Pain Relief
Study 1 | 65% [P<0.05 versus placebo and sumatriptan.] n = 364 | 55% n = 361 | 44% n = 356 | 28% n = 360
Study 2 | 57% n = 362 | 50% n = 362 | 43% n = 364 | 29% n = 382
Sustained Pain Free (2-24 Hours)
Study 1 | 25% [P <0.01 versus placebo, sumatriptan, and naproxen sodium.] n = 364 | 16% n = 361 | 10% n = 356 | 8% n = 360
Study 2 | 23% n = 362 | 14% n = 362 | 10% n = 364 | 7% n = 382

The percentage of patients achieving initial headache pain relief within 2 hours following treatment with TREXIMET 85/500 mg is shown in Figure 1.

Figure 1. Percentage of Adult Patients with Initial Headache Pain Relief within 2 Hours

Compared with placebo, there was a decreased incidence of photophobia, phonophobia, and nausea 2 hours after the administration of TREXIMET 85/500 mg. The estimated probability of taking a rescue medication over the first 24 hours is shown in Figure 2.

Figure 2. Estimated Probability of Adults Taking a Rescue Medication over the 24 Hours following the First Dose [Kaplan-Meier plot based on data obtained in the 2 clinical controlled trials providing evidence of efficacy with patients not using additional treatments censored to 24 hours. Plot also includes patients who had no response to the initial dose. No rescue medication was allowed within 2 hours postdose.]

TREXIMET 85/500 mg was more effective than placebo regardless of the presence of aura; duration of headache prior to treatment; gender, age, or weight of the subject; or concomitant use of oral contraceptives or common migraine prophylactic drugs (e.g., beta-blockers, anti-epileptic drugs, tricyclic antidepressants).

14.2 Pediatric Patients 12 to 17 Years of Age

The efficacy of TREXIMET in the acute treatment of migraine with or without aura in pediatric patients 12 to 17 years of age was demonstrated in a randomized, double-blind, multicenter, parallel-group, placebo-controlled, multicenter trial comparing 3 doses of TREXIMET and placebo (Study 3). Patients enrolled in this trial were mostly female (59%) and white (81%), with a mean age of 15 years.

Patients were required to have at least a 6-month history of migraine attacks with or without aura usually lasting 3 hours or more when untreated. Following a single-blind, placebo run-in phase, placebo nonresponders were randomized to receive a single dose of either TREXIMET 10/60 mg, 30/180 mg, 85/500 mg, or placebo. Patients were instructed to treat a single migraine attack with headache pain of moderate to severe intensity. No rescue medication was allowed within 2 hours postdose. Patients evaluated their headache pain 2 hours after taking 1 dose of study medication. Two-hour pain free was defined as a reduction in headache severity from moderate or severe pain to no pain at 2 hours postdose.

Results are summarized in Table 5. The percentage of patients who were pain free at 2 hours postdose was significantly greater among patients who received any of the 3 doses of TREXIMET compared with placebo.

Table 5. Percentage of Pediatric Patients 12 to 17 Years of Age with 2-Hour Pain-Free Response Following Treatment in Study 3 [P values provided only for prespecified comparisons.]
Endpoint | TREXIMET 10/60 mg (n = 96) | TREXIMET 30/180 mg (n = 97) | TREXIMET 85/500 mg (n = 152) | Placebo (n = 145)
2-Hour Pain Free | 29% [P<0.01 versus placebo.] | 27% | 24% | 10%

The percentage of pediatric patients who remained pain free without use of other medications 2 through 24 hours postdose was significantly greater after administration of a single dose of TREXIMET 85/500 mg compared with placebo. A greater percentage of pediatric patients who received a single dose of 10/60 mg or 30/180 mg remained pain free 2 through 24 hours postdose compared with placebo.

Compared with placebo, the incidence of photophobia and phonophobia was significantly decreased 2 hours after the administration of a single dose of 85/500 mg, whereas, the incidence of nausea was comparable. There was a decreased incidence of photophobia, phonophobia, and nausea 2 hours after single-dose administration of 10/60 mg or 30/180 mg compared with placebo.

16 HOW SUPPLIED/STORAGE AND HANDLING

TREXIMET 85/500 mg contains 119 mg of sumatriptan succinate equivalent to 85 mg of sumatriptan and 500 mg of naproxen sodium and is supplied as blue film-coated tablets debossed on one side with TREXIMET in bottles of 9 tablets with desiccant (NDC 42847-850-09).

TREXIMET 10/60 mg contains 14 mg of sumatriptan succinate equivalent to 10 mg of sumatriptan and 60 mg of naproxen sodium and is supplied as light-blue film-coated tablets debossed on one side with TREXIMET and the other side with 10-60 in bottles of 9 tablets with desiccant (NDC 42847-860-09).

STORAGE AND HANDLING

Store at 25°C (77°F); excursions permitted to 15°-30°C (59°-86°F) [see USP Controlled Room Temperature]. Do not repackage; dispense and store in original container with desiccant.

17 PATIENT COUNSELING INFORMATION

Advise the patient to read the FDA-approved patient labeling (Medication Guide) that accompanies each prescription dispensed. Inform patients, families, or their caregivers of the following information before initiating therapy with TREXIMET and periodically during the course of ongoing therapy.

Cardiovascular Thrombotic Events, Prinzmetal's Angina, Other Vasospasm-Related Events, Arrhythmias and Cerebrovascular Events

Advise patients to be alert for the symptoms of cardiovascular thrombotic effects such as myocardial infarction or stroke, which may result in hospitalization and even death. Although serious cardiovascular events can occur without warning symptoms, patients should be alert for signs and symptoms of chest pain, shortness of breath, weakness, irregular heartbeat, significant rise in blood pressure, weakness and slurring of speech, and should be advised to report any of these symptoms to their health care provider immediately. Apprise patients of the importance of this follow-up [see Warnings and Precautions (5.1, 5.3, 5.5, 5.6, 5.8)].

Gastrointestinal Bleeding, Ulceration, and Perforation

Advise patients to report symptoms of ulcerations and bleeding, including epigastric pain, dyspepsia, melena, and hematemesis to their health care provider. In the setting of concomitant use of low-dose aspirin for cardiac prophylaxis, inform patients of the increased risk for and the signs and symptoms of GI bleeding [see Warnings and Precautions (5.2)].

Hepatotoxicity

Inform patients of the warning signs and symptoms of hepatotoxicity (e.g., nausea, fatigue, lethargy, pruritus, diarrhea, jaundice, right upper quadrant tenderness, and "flu-like" symptoms). If these occur, instruct patients to stop TREXIMET and seek immediate medical therapy [see Warnings and Precautions (5.7)].

Anaphylactic Reactions

Inform patients that anaphylactic reactions have occurred in patients receiving the components of TREXIMET. Such reactions can be life-threatening or fatal. In general, anaphylactic reactions to drugs are more likely to occur in individuals with a history of sensitivity to multiple allergens. Inform patients of the signs of an anaphylactic reaction (e.g., difficulty breathing, swelling of the face or throat). If these occur, patients should be instructed to seek immediate emergency help [see Contraindications (4), Warnings and Precautions (5.13)].

Serious Skin Reactions, including DRESS

Inform patients that TREXIMET, like other NSAID-containing products, may increase the risk of serious skin side effects such as exfoliative dermatitis, Stevens-Johnson syndrome, toxic epidermal necrolysis, and DRESS, which may result in hospitalizations and even death. Although serious skin reactions may occur without warning, patients should be alert for the signs and symptoms of skin rash and blisters, fever, or other signs of hypersensitivity such as itching and should ask for medical advice when observing any indicative signs or symptoms. Advise patients to stop taking TREXIMET immediately if they develop any type of rash or fever and contact their healthcare providers as soon as possible [see Warnings and Precautions (5.14, 5.15)].

Fetal Toxicity

Inform pregnant women to avoid use of TREXIMET and other NSAIDs starting at 30 weeks gestation because of the risk of the premature closing of the fetal ductus arteriosus. If treatment with TREXIMET is needed for a pregnant woman between about 20 to 30 weeks gestation, advise her that she may need to be monitored for oligohydramnios, if treatment continues for longer than 48 hours [see Warnings and Precautions (5.16), Use in Specific Populations (8.1)].

Lactation

Advise patients to notify their healthcare provider if they are breastfeeding or plan to breastfeed [see Use in Specific Populations (8.2)].

Female Fertility

Advise females of reproductive potential who desire pregnancy that NSAIDs, including TREXIMET, may be associated with a reversible delay in ovulation [see Use in Specific Populations (8.3)].

Heart Failure and Edema

Advise patients to be alert for the symptoms of congestive heart failure including shortness of breath, unexplained weight gain, or edema and to contact their healthcare provider if such symptoms occur [see Warnings and Precautions (5.9)].

Concomitant Use with Other Triptans or Ergot Medications

Inform patients that use of TREXIMET within 24 hours of another triptan or an ergot-type medication (including dihydroergotamine or methysergide) is contraindicated [see Contraindications (4), Drug Interactions (7.1)].

Serotonin Syndrome

Caution patients about the risk of serotonin syndrome with the use of TREXIMET or other triptans, particularly during concomitant use with SSRIs, SNRIs, TCAs, and MAO inhibitors [see Warnings and Precautions (5.11), Drug Interactions (7.1)].

Medication Overuse Headache

Inform patients that use of acute migraine drugs for 10 or more days per month may lead to an exacerbation of headache and encourage patients to record headache frequency and drug use (e.g., by keeping a headache diary) [see Warnings and Precautions (5.10)].

Ability to Perform Complex Tasks

Treatment with TREXIMET may cause somnolence and dizziness; instruct patients to evaluate their ability to perform complex tasks after administration of TREXIMET [see Adverse Reactions (6.1)].

Asthma

Advise patients with preexisting asthma to seek immediate medical attention if their asthma worsens after taking TREXIMET. Patients with a history of aspirin-sensitive asthma should not take TREXIMET [see Contraindications (4), Warnings and Precautions (5.18)].

Avoid Concomitant Use of NSAIDs

Inform patients that the concomitant use of TREXIMET with other NSAIDs or salicylates (e.g., diflunisal, salsalate) is not recommended due to the increased risk of gastrointestinal toxicity, and little or no increase in efficacy [see Warnings and Precautions (5.2) and Drug Interactions (7)]. Alert patients that NSAIDs may be present in "over the counter" medications for treatment of colds, fever, or insomnia.

Use of NSAIDS and Low-Dose Aspirin

Inform patients not to use low-dose aspirin concomitantly with TREXIMET until they talk to their healthcare provider [see Drug Interactions (7)].

TREXIMET is a registered trademark of Currax™ Pharmaceuticals LLC. The other brands listed are trademarks of their respective owners and are not trademarks of Currax™ Pharmaceuticals LLC. The makers of these brands are not affiliated with and do not endorse Currax™ Pharmaceuticals LLC or its products.

Distributed by Currax™ Pharmaceuticals LLC
Brentwood, TN 37027

© 2024 Currax™ Pharmaceuticals LLC. All rights reserved.

TRE-LC003.10

MEDICATION GUIDE
TREXIMET® [trex' i-met] Tablets
(sumatriptan and naproxen sodium)

Read this Medication Guide before you start taking TREXIMET and each time you get a refill. There may be new information. This Medication Guide does not take the place of talking with your healthcare provider about your medical condition or treatment.

What is the most important information I should know about TREXIMET?
TREXIMET may increase your chance of a heart attack or stroke that can lead to death. TREXIMET contains 2 medicines: sumatriptan and naproxen sodium (a nonsteroidal anti-inflammatory drug [NSAID]).

- This risk may happen early in treatment and may increase:

- with increasing doses of NSAIDs
- with longer use of NSAIDs

Do not take TREXIMET right before or after a heart surgery called a "coronary artery bypass graft (CABG)."
Avoid taking TREXIMET after a recent heart attack, unless your healthcare provider tells you to. You may have an increased risk of another heart attack if you take NSAIDs after a recent heart attack.
Stop taking TREXIMET and get emergency help right away if you have any of the following symptoms of a heart attack or stroke:

- discomfort in the center of your chest that lasts for more than a few minutes, or that goes away and comes back
- severe tightness, pain, pressure, or heaviness in your chest, throat, neck, or jaw
- pain or discomfort in your arms, back, neck, jaw, or stomach
- shortness of breath with or without chest discomfort
- breaking out in a cold sweat
- nausea or vomiting
- feeling lightheaded
- weakness in one part or on one side of your body
- slurred speech

TREXIMET is not for people with risk factors for heart disease unless a heart exam is done and shows no problem. You have a higher risk for heart disease if you:

- have high blood pressure
- smoke
- have diabetes

- have high cholesterol levels
- are overweight
- have a family history of heart disease

TREXIMET can cause ulcers and bleeding in the stomach and intestines at any time during your treatment.
Ulcers and bleeding can happen without warning symptoms and may cause death.
Your chance of getting an ulcer or bleeding increases with:

- past history of stomach ulcers, or stomach or intestinal bleeding with use of NSAIDs
- the use of medicines called "corticosteroids," "anticoagulants," and antidepressant medicines called "SSRIs" or "SNRIs"
- more frequent use
- drinking alcohol
- having poor health
- advanced liver disease
- bleeding problems

- longer use
- smoking
- older age

TREXIMET may cause serious allergic reactions or serious skin reactions that can be life-threatening. Stop taking TREXIMET and get emergency help right away if you develop:

- sudden wheezing
- rash
- problems breathing or swallowing
- blisters or bleeding of your lips, eye lids, mouth, nose, or genitals

- swelling of your lips, tongue, throat or body
- fainting
- reddening of your skin with blisters or peeling

TREXIMET should only be used exactly as prescribed, at the lowest dose possible for your treatment, and for the shortest time needed.
TREXIMET already contains an NSAID (naproxen). Do not use TREXIMET with other medicines to lessen pain or fever or with other medicines for colds or sleeping problems without talking to your healthcare provider first, because they may contain an NSAID also.

What is TREXIMET?
TREXIMET is a prescription medicine that contains sumatriptan and naproxen sodium (an NSAID). TREXIMET is used to treat acute migraine headaches with or without aura in patients 12 years of age and older.
TREXIMET is not used to treat other types of headaches such as hemiplegic (that make you unable to move on one side of your body) or basilar (rare form of migraine with aura) migraines.
TREXIMET is not used to prevent or decrease the number of migraine headaches you have.
It is not known if TREXIMET is safe and effective to treat cluster headaches.

Who should not take TREXIMET?
Do not take TREXIMET if you have:

- heart problems, history of heart problems, or right before or after heart bypass surgery
- had a stroke, transient ischemic attack (TIAs), or problems with your blood circulation
- hemiplegic migraines or basilar migraines. If you are not sure if you have these types of migraines, ask your healthcare provider.
- narrowing of blood vessels to your legs and arms (peripheral vascular disease), stomach (ischemic bowel disease), or kidneys
- uncontrolled high blood pressure
- taken any medicines in the last 24 hours that are called 5-HT1 agonists that are triptans or contain ergotamine. Ask your healthcare provider for a list of these medicines if you are not sure.
- taken an antidepressant medicine called a monoamine oxidase (MAO) inhibitor within the last 2 weeks. Ask your healthcare provider for a list if you are not sure.
- had an asthma attack, hives, or other allergic reaction with aspirin or any other NSAID medicine
- an allergy to sumatriptan, naproxen, or any of the ingredients in TREXIMET. See "What are the ingredients in TREXIMET?" below for a complete list of ingredients.
- liver problems

What should I tell my healthcare provider before taking TREXIMET?
Before you take TREXIMET, tell your healthcare provider about all of your medical conditions, including if you:

- have high blood pressure
- have asthma
- have high cholesterol
- have diabetes
- smoke
- are overweight
- have heart problems or a family history of heart problems or stroke
- have kidney problems
- have liver problems
- have had epilepsy or seizures
- are not using effective birth control
- are pregnant, think you might be pregnant, or are trying to become pregnant. Taking NSAIDs, including TREXIMET, at about 20 weeks of pregnancy or later may harm your unborn baby. If you need to take NSAIDs for more than 2 days when you are between 20 and 30 weeks of pregnancy, your healthcare provider may need to monitor the amount of fluid in your womb around your baby. You should not take NSAIDs after about 30 weeks of pregnancy.
- are breastfeeding or plan to breastfeed. The components of TREXIMET pass into your breast milk and may harm your baby. Talk with your healthcare provider about the best way to feed your baby if you take TREXIMET.

Tell your healthcare provider about all the medicines you take, including prescription and over-the-counter medicines, vitamins, and herbal supplements.
TREXIMET and certain other medicines can affect each other, causing serious side effects.

How should I take TREXIMET?

- Certain people should take their first dose of TREXIMET in their healthcare provider's office or in another medical setting. Ask your healthcare provider if you should take your first dose in a medical setting.
- Take TREXIMET exactly as your healthcare provider tells you to take it.
- Take TREXIMET tablets whole with water or other liquids.
- TREXIMET can be taken with or without food.
- If you do not get any relief after your first dose, do not take a second dose without first talking with your healthcare provider.
- If your headache comes back or you only get some relief from your headache:
  - For adults: a second dose may be taken 2 hours after the first dose. Do not take more than 2 doses of TREXIMET 85/500 mg in a 24-hour period.
  - For children 12 to 17 years of age: it is not known if taking more than 1 dose of TREXIMET in 24 hours is safe and effective. Talk to your healthcare provider about what to do if your headache does not go away or comes back.
- If you take too much TREXIMET, call your healthcare provider or go to the nearest hospital emergency room right away.
- You should write down when you have headaches and when you take TREXIMET so you can talk with your healthcare provider about how TREXIMET is working for you.

What should I avoid while taking TREXIMET?
TREXIMET can cause dizziness, weakness, or drowsiness. If you have these symptoms, do not drive a car, use machinery, or do anything where you need to be alert.

What are the possible side effects of TREXIMET?
TREXIMET may cause serious side effects. See "What is the most important information I should know about TREXIMET?"
These serious side effects include:

- changes in color or sensation in your fingers and toes (Raynaud's syndrome)
- new or worse high blood pressure
- heart failure from body swelling (fluid retention)
- kidney problems including kidney failure
- low red blood cells (anemia)
- liver problems including liver failure
- asthma attacks in people who have asthma
- stomach and intestinal problems (gastrointestinal and colonic ischemic events). Symptoms of gastrointestinal and colonic ischemic events include:

- sudden or severe stomach pain
- weight loss
- constipation or diarrhea
- fever

- stomach pain after meals
- nausea or vomiting
- bloody diarrhea

- problems with blood circulation to your legs and feet (peripheral vascular ischemia). Symptoms of peripheral vascular ischemia include:

- cramping and pain in your legs or hips
- feeling of heaviness or tightness in your leg muscles
- burning or aching pain in your feet or toes while resting
- numbness, tingling, or weakness in your legs
- cold feeling or color changes in 1 or both legs or feet

- medication overuse headaches. Some people who use too many TREXIMET tablets may have worse headaches (medication overuse headache). If your headaches get worse, your healthcare provider may decide to stop your treatment with TREXIMET.
- serotonin syndrome. Serotonin syndrome is a rare but serious problem that can happen in people using TREXIMET, especially if TREXIMET is used with antidepressant medicines called SSRIs or SNRIs.
  Stop taking TREXIMET and call your healthcare provider right away if you have any of the following symptoms of serotonin syndrome:

- changes in blood pressure
- tight muscles
- mental changes such as seeing things that are not there (hallucinations), agitation, or coma

- fast heartbeat
- high body temperature
- trouble walking

- seizures. Seizures have happened in people taking sumatriptan, one of the ingredients in TREXIMET, who have never had seizures before. Talk with your healthcare provider about your chance of having seizures while you take TREXIMET.

The most common side effects of TREXIMET include:

- dizziness
- pain, discomfort, or stiffness in your neck, throat, jaw, or chest
- tingling or numbness in your fingers or toes
- dry mouth
- heartbeat problems

- feeling weak, drowsy, or tired
- nausea
- heartburn
- feeling hot
- muscle tightness

Stop TREXIMET and call your healthcare provider right away if you have any of the following symptoms:

- nausea that seems out of proportion to your migraine
- vomit blood
- yellow skin or eyes
- more tired or weaker than usual
- itching
- swelling of the arms, legs, hands, and feet

- sudden or severe stomach pain
- blood in your bowel movement or it is black and sticky like tar
- unusual weight gain
- flu-like symptoms
- diarrhea
- tenderness in your upper right side

Tell your healthcare provider if you have any side effects that bother you or do not go away.
These are not all of the side effects of TREXIMET. For more information, ask your healthcare provider or pharmacist.
Call your doctor for medical advice about side effects. You may report side effects to FDA at 1-800-FDA-1088.

How should I store TREXIMET?
Store TREXIMET at room temperature between 68°F to 77°F (20°C to 25°C).
Keep TREXIMET and all medicines out of the reach of children.

General information about the safe and effective use of TREXIMET
Medicines are sometimes prescribed for purposes other than those listed in a Medication Guide. Do not use TREXIMET for a condition for which it was not prescribed. Do not give TREXIMET to other people, even if they have the same problem you have. It may harm them.
This Medication Guide summarizes the most important information about TREXIMET. If you would like more information, talk with your healthcare provider. You can ask your healthcare provider or pharmacist for information about TREXIMET that is written for healthcare professionals.
For more information call 1-800-793-2145 or visit www.TREXIMET.com.

What are the ingredients in TREXIMET?
Active ingredients: sumatriptan succinate and naproxen sodium.
Inactive ingredients in all strengths: croscarmellose sodium, dibasic calcium phosphate, FD&C Blue No. 2, magnesium stearate, microcrystalline cellulose, povidone, sodium bicarbonate, talc, and titanium dioxide.
85/500-mg tablets also contain: hypromellose and triacetin.
10/60-mg tablets also contain: polyethylene glycol and polyvinyl alcohol.
TREXIMET is a registered trademark of Currax™ Pharmaceuticals LLC. The other brands listed are trademarks of their respective owners and are not trademarks of Currax™ Pharmaceuticals LLC. The makers of these brands are not affiliated with and do not endorse Currax™ Pharmaceuticals LLC or its products.
TRE-LC006.08
Distributed by Currax™ Pharmaceuticals LLC;
Brentwood, TN 37027 © 2024 Currax™ Pharmaceuticals LLC.
All rights reserved.

This Medication Guide has been approved by the U.S. Food and Drug Administration.

Revised: 02/2024

PRINCIPAL DISPLAY PANEL - 85 mg/500 mg Tablet Bottle Label

NDC 42847-850-09

Rx only

Treximet®
sumatriptan/naproxen sodium Tablets

85 mg/500 mg

Do not repackage; dispense and store
in original container.

Dispense the accompanying
Medication Guide to each patient.

9 Tablets